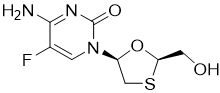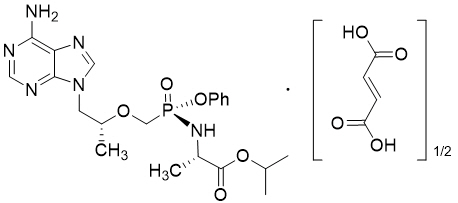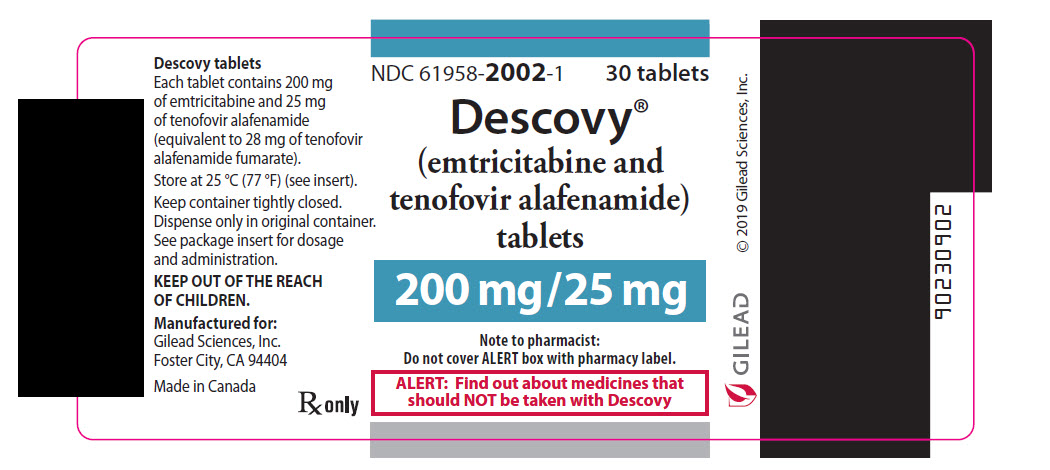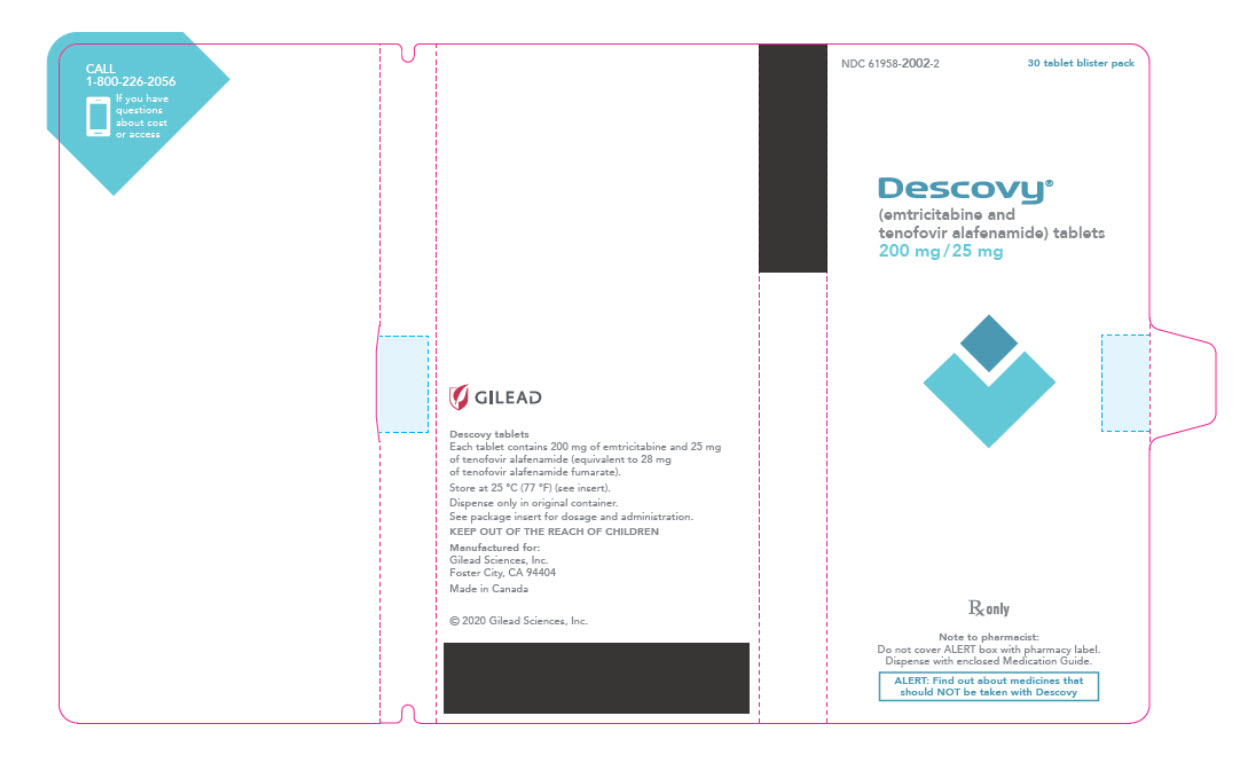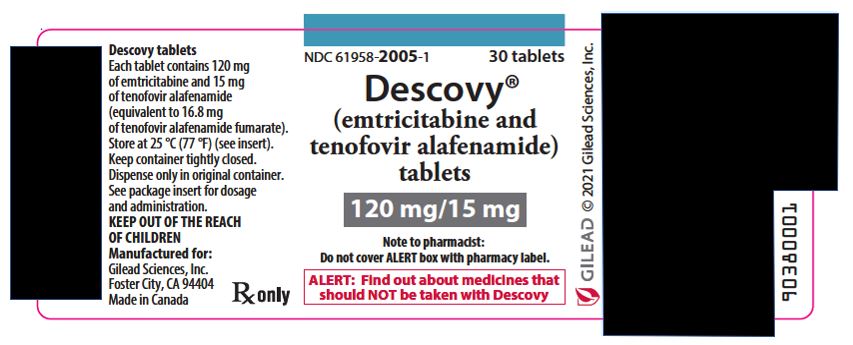 DRUG LABEL: DESCOVY
NDC: 61958-2002 | Form: TABLET
Manufacturer: Gilead Sciences, Inc.
Category: prescription | Type: HUMAN PRESCRIPTION DRUG LABEL
Date: 20250620

ACTIVE INGREDIENTS: EMTRICITABINE 200 mg/1 1; TENOFOVIR ALAFENAMIDE FUMARATE 25 mg/1 1
INACTIVE INGREDIENTS: MICROCRYSTALLINE CELLULOSE; CROSCARMELLOSE SODIUM; MAGNESIUM STEARATE; WATER; POLYVINYL ALCOHOL, UNSPECIFIED; TITANIUM DIOXIDE; POLYETHYLENE GLYCOL 3350; TALC; FD&C BLUE NO. 2

HIGHLIGHTS OF PRESCRIBING INFORMATION

These highlights do not include all the information needed to use DESCOVY safely and effectively. See full prescribing information for DESCOVY.
DESCOVY® (emtricitabine and tenofovir alafenamide) tablets, for oral use
Initial U.S. Approval: 2015

WARNING: POST-TREATMENT ACUTE EXACERBATION OF HEPATITIS B and RISK OF DRUG RESISTANCE WITH USE OF DESCOVY FOR HIV-1 PRE-EXPOSURE PROPHYLAXIS (PrEP) IN UNDIAGNOSED EARLY HIV-1 INFECTION

See full prescribing information for complete boxed warning.

Severe acute exacerbations of hepatitis B (HBV) have been reported in individuals with HBV who have discontinued products containing emtricitabine (FTC) and/or tenofovir disoproxil fumarate (TDF), and may occur with discontinuation of DESCOVY. Hepatic function should be monitored closely in these individuals. If appropriate, anti-hepatitis B therapy may be warranted. (5.1)

DESCOVY used for HIV-1 PrEP must only be prescribed to individuals confirmed to be HIV-negative immediately prior to initiating and at least every 3 months during use. Drug-resistant HIV-1 variants have been identified with use of FTC/TDF for HIV-1 PrEP following undetected acute HIV-1 infection. Do not initiate DESCOVY for HIV-1 PrEP if signs or symptoms of acute HIV-1 infection are present unless negative infection status is confirmed. (5.2)

RECENT MAJOR CHANGES

Indications and Usage (1.1) | 06/2025
Dosage and Administration, Recommended Dosage for Treatment of HIV-1 Infection in Pediatric Patients Weighing at Least 14 kg to Less than 35 kg (2.4) | 06/2025

1 INDICATIONS AND USAGE

HIV-1 Treatment (1.1):

DESCOVY is a two-drug combination of emtricitabine (FTC) and tenofovir alafenamide (TAF), both HIV nucleoside analog reverse transcriptase inhibitors (NRTIs), and is indicated:

- in combination with other antiretroviral agents for the treatment of HIV-1 infection in adults and adolescent patients weighing at least 35 kg.
- for the treatment of HIV-1 infection in pediatric patients weighing at least 14 kg to less than 35 kg in combination with other antiretroviral agents, including darunavir and cobicistat but not other protease inhibitors that require a CYP3A inhibitor.

HIV-1 PrEP (1.2):

DESCOVY is indicated in at-risk adults and adolescents weighing at least 35 kg for pre-exposure prophylaxis (PrEP) to reduce the risk of HIV-1 infection from sexual acquisition, excluding individuals at risk from receptive vaginal sex. Individuals must have a negative HIV-1 test immediately prior to initiating DESCOVY for HIV-1 PrEP.

Limitations of Use (1.2):

The indication does not include use of DESCOVY in individuals at risk of HIV-1 from receptive vaginal sex because effectiveness in this population has not been evaluated.

2 DOSAGE AND ADMINISTRATION

- Testing: Prior to or when initiating DESCOVY, test for hepatitis B virus infection. Prior to or when initiating DESCOVY, and during use on a clinically appropriate schedule, assess serum creatinine, estimated creatinine clearance, urine glucose, and urine protein in all individuals. In individuals with chronic kidney disease, also assess serum phosphorus. (2.1)
- HIV-1 Screening: Screen all individuals for HIV-1 infection immediately prior to initiating DESCOVY for HIV-1 PrEP and at least once every 3 months while taking DESCOVY, and upon diagnosis of any other sexually transmitted infections (STIs). (2.2)
- Recommended dosage:
  - Treatment of HIV-1 Infection:
    - Adult and pediatric patients weighing at least 35 kg: One 200 mg/25 mg tablet once daily with or without food. (2.3)
    - Pediatric patients receiving DESCOVY with other antiretroviral agents, including darunavir and cobicistat but not other protease inhibitors administered with either ritonavir or cobicistat, and weighing:
      - at least 25 to less than 35 kg: One 200 mg/25 mg tablet once daily with or without food. (2.4)
      - at least 14 to less than 25 kg: One 120 mg/15 mg tablet once daily with or without food. (2.4)
  - HIV-1 PrEP: One 200 mg/25 mg tablet once daily with or without food in individuals with body weight at least 35 kg. (2.5)
- Renal impairment: DESCOVY is not recommended in individuals with estimated creatinine clearance of 15 to below 30 mL per minute, or below 15 mL per minute who are not receiving chronic hemodialysis. (2.6)

3 DOSAGE FORMS AND STRENGTHS

Tablets: 200 mg/25 mg and 120 mg/15 mg of FTC and TAF respectively (3)

4 CONTRAINDICATIONS

DESCOVY for HIV-1 PrEP is contraindicated in individuals with unknown or positive HIV-1 status. (4)

5 WARNINGS AND PRECAUTIONS

- Comprehensive management to reduce the risk of sexually transmitted infections (STIs), including HIV-1, when DESCOVY is used for HIV-1 PrEP: Counsel on adherence to daily dosing and safer sex practices, including condoms, to reduce the risk of STIs. (5.2)
- Management to reduce the risk of acquiring HIV-1 drug resistance when DESCOVY is used for HIV-1 PrEP: refer to full prescribing information for additional detail. (5.2)
- Immune reconstitution syndrome during treatment of HIV-1 infection: May necessitate further evaluation and treatment. (5.3)
- New onset or worsening renal impairment: Assess serum creatinine, estimated creatinine clearance, urine glucose, and urine protein when initiating DESCOVY and during use on a clinically appropriate schedule in all individuals. Also assess serum phosphorus in individuals with chronic kidney disease. (5.4)
- Lactic acidosis/severe hepatomegaly with steatosis: Discontinue DESCOVY in individuals who develop symptoms or laboratory findings suggestive of lactic acidosis or pronounced hepatotoxicity. (5.5)

6 ADVERSE REACTIONS

- In participants with HIV-1, the most common adverse reaction (incidence greater than or equal to 10%, all grades) was nausea. (6.1)
- In adults without HIV-1 in a PrEP trial, the most common adverse reaction (incidence greater than or equal to 5%, all grades) was diarrhea. (6.1)

To report SUSPECTED ADVERSE REACTIONS, contact Gilead Sciences, Inc. at 1-800-GILEAD-5 or FDA at 1-800-FDA-1088 or www.fda.gov/medwatch.

7 DRUG INTERACTIONS

Consult the Full Prescribing Information prior to and during use for potential drug interactions. (7, 12.3)

8 USE IN SPECIFIC POPULATIONS

- Pediatrics:
  - Treatment of HIV-1 Infection: Not recommended for patients weighing less than 14 kg. (8.4)
  - HIV-1 PrEP: Not recommended for individuals weighing less than 35 kg. (8.4)

FULL PRESCRIBING INFORMATION

WARNING: POST-TREATMENT ACUTE EXACERBATION OF HEPATITIS B and RISK OF DRUG RESISTANCE WITH USE OF DESCOVY FOR HIV-1 PRE-EXPOSURE PROPHYLAXIS (PrEP) IN UNDIAGNOSED EARLY HIV-1 INFECTION

Severe acute exacerbations of hepatitis B (HBV) have been reported in individuals with HBV who have discontinued products containing emtricitabine (FTC) and/or tenofovir disoproxil fumarate (TDF) and may occur with discontinuation of DESCOVY.

Hepatic function should be monitored closely with both clinical and laboratory follow-up for at least several months in individuals with HBV who discontinue DESCOVY. If appropriate, anti-hepatitis B therapy may be warranted [see Warnings and Precautions (5.1)].

DESCOVY used for HIV-1 PrEP must only be prescribed to individuals confirmed to be HIV-negative immediately prior to initiating and at least every 3 months during use. Drug-resistant HIV-1 variants have been identified with use of FTC/TDF for HIV-1 PrEP following undetected acute HIV-1 infection. Do not initiate DESCOVY for HIV-1 PrEP if signs or symptoms of acute HIV-1 infection are present unless negative infection status is confirmed [see Warnings and Precautions (5.2)].

1 INDICATIONS AND USAGE

1.1 Treatment of HIV-1 Infection

DESCOVY is indicated in combination with other antiretroviral agents for the treatment of HIV-1 infection in adults and adolescent patients weighing at least 35 kg.

DESCOVY is indicated for the treatment of HIV-1 infection in pediatric patients weighing at least 14 kg to less than 35 kg in combination with other antiretroviral agents, including darunavir and cobicistat but not other protease inhibitors that require a CYP3A inhibitor.

1.2 HIV-1 Pre-Exposure Prophylaxis (PrEP)

DESCOVY is indicated in at-risk adults and adolescents weighing at least 35 kg for pre-exposure prophylaxis (PrEP) to reduce the risk of HIV-1 infection from sexual acquisition, excluding individuals at risk from receptive vaginal sex. Individuals must have a negative HIV-1 test immediately prior to initiating DESCOVY for HIV-1 PrEP [see Dosage and Administration (2.2) and Warnings and Precautions (5.2)].

Limitations of Use:

The indication does not include use of DESCOVY in individuals at risk of HIV-1 from receptive vaginal sex because effectiveness in this population has not been evaluated [see Clinical Studies (14.3)].

2 DOSAGE AND ADMINISTRATION

2.1 Testing When Initiating and During Use of DESCOVY for Treatment of HIV-1 Infection or for HIV-1 PrEP

Prior to or when initiating DESCOVY, test individuals for hepatitis B virus infection [see Warnings and Precautions (5.1)].

Prior to or when initiating DESCOVY, and during use of DESCOVY on a clinically appropriate schedule, assess serum creatinine, estimated creatinine clearance, urine glucose, and urine protein in all individuals. In individuals with chronic kidney disease, also assess serum phosphorus [see Warnings and Precautions (5.4)].

2.2 HIV-1 Screening for Individuals Receiving DESCOVY for HIV-1 PrEP

Screen all individuals for HIV-1 infection immediately prior to initiating DESCOVY for HIV-1 PrEP and at least once every 3 months while taking DESCOVY, and upon diagnosis of any other sexually transmitted infections (STIs) [see Indications and Usage (1.2), Contraindications (4), and Warnings and Precautions (5.2)].

If recent (<1 month) exposures to HIV-1 are suspected or clinical symptoms consistent with acute HIV-1 infection are present, use a test approved or cleared by the FDA as an aid in the diagnosis of acute or primary HIV-1 infection [see Warnings and Precautions (5.2), Use in Specific Populations (8.4), and Clinical Studies (14.3)].

2.3 Recommended Dosage for Treatment of HIV-1 Infection in Adults and Pediatric Patients Weighing at Least 35 kg

DESCOVY is a two-drug fixed dose combination product containing emtricitabine (FTC) and tenofovir alafenamide (TAF).

The recommended dosage of DESCOVY for treatment of HIV-1 is one tablet containing 200 mg FTC and 25 mg of TAF taken orally once daily with or without food in:

- adults and pediatric patients with body weight at least 35 kg and estimated creatinine clearance greater than or equal to 30 mL per minute; or
- adults with creatinine clearance below 15 mL per minute who are receiving chronic hemodialysis. On days of hemodialysis, administer the daily dose of DESCOVY after completion of hemodialysis treatment [see Use in Specific Populations (8.6) and Clinical Pharmacology (12.3)].

The safety and effectiveness of DESCOVY coadministered with an HIV-1 protease inhibitor that is administered with either ritonavir or cobicistat have not been established in adults with creatinine clearance below 15 mL per minute, with or without hemodialysis.

For specific dosing recommendations for coadministered antiretroviral drugs, refer to their respective prescribing information [see Drug Interactions (7)].

2.4 Recommended Dosage for Treatment of HIV-1 Infection in Pediatric Patients Weighing at Least 14 kg to Less than 35 kg

The recommended dosage of DESCOVY for treatment of HIV-1 in pediatric patients is based on body weight and is provided in Table 1. This dosing information is applicable to pediatric patients with estimated creatinine clearance greater than or equal to 30 mL per minute [see Use in Specific Populations (8.6) and Clinical Pharmacology (12.3)] who are receiving DESCOVY with other antiretroviral agents, including darunavir (DRV) and cobicistat (COBI) but not including other HIV-1 protease inhibitors that are administered with either ritonavir or cobicistat.

Table 1 Dosing for Treatment of HIV-1 Infection in Pediatric Patients Weighing 14 to Less than 35 kg
Body Weight (kg) | DESCOVY Dosage
25 kg to less than 35 kg | One tablet containing 200 mg of FTC and 25 mg of TAF taken orally once daily
14 kg to less than 25 kg | One tablet containing 120 mg of FTC and 15 mg of TAF taken orally once daily

For specific dosing recommendations for coadministered antiretroviral drugs, refer to their respective prescribing information [see Drug Interactions (7)].

2.5 Recommended Dosage for HIV-1 PrEP in Adults and Adolescents Weighing at Least 35 kg

The dosage of DESCOVY for HIV-1 PrEP is one tablet (containing 200 mg of FTC and 25 mg of TAF) once daily taken orally with or without food in:

- adults and adolescents without HIV-1 weighing at least 35 kg and with a creatinine clearance greater than or equal to 30 mL per minute; or
- adults without HIV-1 and with creatinine clearance below 15 mL per minute who are receiving chronic hemodialysis. On days of hemodialysis, administer the daily dose of DESCOVY after completion of hemodialysis treatment [see Indications and Usage (1.2) and Clinical Pharmacology (12.3)].

2.6 Not Recommended in Individuals with Severe Renal Impairment for Treatment of HIV-1 Infection or for HIV-1 PrEP

DESCOVY is not recommended in individuals with:

- severe renal impairment (estimated creatinine clearance of 15 to below 30 mL per minute); or
- end stage renal disease (ESRD; estimated creatinine clearance below 15 mL per minute) who are not receiving chronic hemodialysis [see Dosage and Administration (2.3, 2.5) and Use in Specific Populations (8.6)].

3 DOSAGE FORMS AND STRENGTHS

DESCOVY tablets are available in two dose strengths:

- 200 mg/25 mg tablets: 200 mg of emtricitabine (FTC) and 25 mg of tenofovir alafenamide (TAF) (equivalent to 28 mg of tenofovir alafenamide fumarate). These tablets are blue, rectangular-shaped, film-coated, debossed with “GSI” on one side and “225” on the other side.
- 120 mg/15 mg tablets: 120 mg of FTC and 15 mg of TAF (equivalent to 16.8 mg of tenofovir alafenamide fumarate). These tablets are white, round-shaped, film coated, debossed with “GSI” on one side and “15” on the other side.

4 CONTRAINDICATIONS

DESCOVY for HIV-1 PrEP is contraindicated in individuals with unknown or positive HIV-1 status [see Warnings and Precautions (5.2)].

5 WARNINGS AND PRECAUTIONS

5.1 Severe Acute Exacerbation of Hepatitis B in Individuals with HBV

All individuals should be tested for the presence of hepatitis B virus (HBV) before or when initiating DESCOVY [see Dosage and Administration (2.1)].

Severe acute exacerbations of hepatitis B (e.g., liver decompensation and liver failure) have been reported in individuals with HBV who have discontinued products containing FTC and/or tenofovir disoproxil fumarate (TDF) and may occur with discontinuation of DESCOVY. Individuals with HBV who discontinue DESCOVY should be closely monitored with both clinical and laboratory follow-up for at least several months after stopping treatment. If appropriate, anti-hepatitis B therapy may be warranted, especially in individuals with advanced liver disease or cirrhosis, since post-treatment exacerbation of hepatitis may lead to hepatic decompensation and liver failure. Individuals without HBV should be offered vaccination.

5.2 Comprehensive Management to Reduce the Risk of Sexually Transmitted Infections, Including HIV-1, and Development of HIV-1 Resistance When DESCOVY Is Used for HIV-1 PrEP

Use DESCOVY for HIV-1 PrEP to reduce the risk of HIV-1 infection as part of a comprehensive prevention strategy, including adherence to daily administration and safer sex practices, including condoms, to reduce the risk of sexually transmitted infections (STIs). The time from initiation of DESCOVY for HIV-1 PrEP to maximal protection against HIV-1 infection is unknown.

Risk for HIV-1 acquisition includes behavioral, biological, or epidemiologic factors including but not limited to condomless sex, past or current STIs, self-identified HIV risk, having sexual partners of unknown HIV-1 viremic status, or sexual activity in a high prevalence area or network.

Counsel individuals on the use of other prevention measures (e.g., consistent and correct condom use, knowledge of partner(s)’ HIV-1 status, including viral suppression status, regular testing for STIs that can facilitate HIV-1 transmission). Inform individuals without HIV-1 about, and support their efforts in, reducing sexual risk behavior.

Use DESCOVY to reduce the risk of acquiring HIV-1 only in individuals confirmed to be HIV-1 negative. HIV-1 resistance substitutions may emerge in individuals with undetected HIV-1 infection who are taking only DESCOVY, because DESCOVY alone does not constitute a complete regimen for HIV-1 treatment [see Microbiology (12.4)]; therefore, care should be taken to minimize the risk of initiating or continuing DESCOVY before confirming the individual is HIV-1 negative.

- Some HIV-1 tests only detect anti-HIV antibodies and may not identify HIV-1 during the acute stage of infection. Prior to initiating DESCOVY for HIV-1 PrEP, ask seronegative individuals about recent (in past month) potential exposure events (e.g., condomless sex or condom breaking during sex with a partner of unknown HIV-1 status or unknown viremic status, or a recent STI), and evaluate for current or recent signs or symptoms consistent with acute HIV-1 infection (e.g., fever, fatigue, myalgia, skin rash).
- If recent (<1 month) exposures to HIV-1 are suspected or clinical symptoms consistent with acute HIV-1 infection are present, use a test approved or cleared by the FDA as an aid in the diagnosis of acute or primary HIV-1 infection.

While using DESCOVY for HIV-1 PrEP, HIV-1 testing should be repeated at least every 3 months, and upon diagnosis of any other STIs.

- If an HIV-1 test indicates possible HIV-1 infection, or if symptoms consistent with acute HIV-1 infection develop following a potential exposure event, convert the HIV-1 PrEP regimen to an HIV treatment regimen until negative infection status is confirmed using a test approved or cleared by the FDA as an aid in the diagnosis of acute or primary HIV-1 infection.

Counsel individuals without HIV-1 to strictly adhere to the once daily DESCOVY dosing schedule. The effectiveness of DESCOVY in reducing the risk of acquiring HIV-1 is strongly correlated with adherence, as demonstrated by measurable drug levels in a clinical trial of DESCOVY for HIV-1 PrEP. Some individuals, such as adolescents, may benefit from more frequent visits and counseling to support adherence [see Use in Specific Populations (8.4), Microbiology (12.4), and Clinical Studies (14.3)].

5.3 Immune Reconstitution Syndrome

Immune reconstitution syndrome has been reported in patients with HIV-1 treated with combination antiretroviral therapy, including FTC, a component of DESCOVY. During the initial phase of combination antiretroviral treatment, patients with HIV-1 whose immune system responds may develop an inflammatory response to indolent or residual opportunistic infections (such as Mycobacterium avium infection, cytomegalovirus, Pneumocystis jirovecii pneumonia [PCP], or tuberculosis), which may necessitate further evaluation and treatment.

Autoimmune disorders (such as Graves’ disease, polymyositis, Guillain-Barré syndrome, and autoimmune hepatitis) have also been reported to occur in the setting of immune reconstitution; however, the time to onset is more variable, and can occur many months after initiation of treatment.

5.4 New Onset or Worsening Renal Impairment

Postmarketing cases of renal impairment, including acute renal failure, proximal renal tubulopathy (PRT), and Fanconi syndrome have been reported with TAF-containing products; while most of these cases were characterized by potential confounders that may have contributed to the reported renal events, it is also possible these factors may have predisposed patients to tenofovir-related adverse events [see Adverse Reactions (6.1, 6.2)]. DESCOVY is not recommended in individuals with estimated creatinine clearance of 15 to below 30 mL per minute, or in individuals with estimated creatinine clearance below 15 mL per minute who are not receiving chronic hemodialysis.

Individuals taking tenofovir prodrugs who have impaired renal function and those taking nephrotoxic agents including non-steroidal anti-inflammatory drugs are at increased risk of developing renal-related adverse reactions.

Prior to or when initiating DESCOVY, and during treatment with DESCOVY on a clinically appropriate schedule, assess serum creatinine, estimated creatinine clearance, urine glucose, and urine protein in all individuals. In individuals with chronic kidney disease, also assess serum phosphorus. Discontinue DESCOVY in individuals who develop clinically significant decreases in renal function or evidence of Fanconi syndrome.

5.5 Lactic Acidosis/Severe Hepatomegaly with Steatosis

Lactic acidosis and severe hepatomegaly with steatosis, including fatal cases, have been reported with the use of nucleoside analogs, including emtricitabine, a component of DESCOVY, and tenofovir DF, another prodrug of tenofovir, alone or in combination with other antiretrovirals. Treatment with DESCOVY should be suspended in any individual who develops clinical or laboratory findings suggestive of lactic acidosis or pronounced hepatotoxicity (which may include hepatomegaly and steatosis even in the absence of marked transaminase elevations).

6 ADVERSE REACTIONS

The following adverse reactions are discussed in other sections of the labeling:

- Severe Acute Exacerbations of Hepatitis B [see Warnings and Precautions (5.1)].
- Immune Reconstitution Syndrome [see Warnings and Precautions (5.3)].
- New Onset or Worsening Renal Impairment [see Warnings and Precautions (5.4)].
- Lactic Acidosis/Severe Hepatomegaly with Steatosis [see Warnings and Precautions (5.5)].

6.1 Clinical Trials Experience

Because clinical trials are conducted under widely varying conditions, adverse reaction rates observed in the clinical trials of a drug (or a drug given in various combinations with other concomitant therapy) cannot be directly compared to rates in the clinical trials of another drug (or drug given in the same or different combination therapy) and may not reflect the rates observed in practice.

Adverse Reactions in Clinical Trials of FTC+TAF with Elvitegravir (EVG) plus Cobicistat (COBI) in Treatment-Naïve Adults with HIV-1

In pooled 48-week trials of antiretroviral treatment-naïve adult participants with HIV-1, the most common adverse reaction in participants treated with FTC+TAF with EVG+COBI (N=866) (incidence greater than or equal to 10%, all grades) was nausea (10%). In this treatment group, 0.9% of participants discontinued FTC+TAF with EVG+COBI due to adverse events during the 48-week treatment period [see Clinical Studies (14.2)]. The safety profile was similar in virologically-suppressed adults with HIV-1 who were switched to FTC+TAF with EVG+COBI (N=799). Antiretroviral treatment-naïve adult participants with HIV-1 treated with FTC+TAF with EVG+COBI experienced mean increases of 30 mg/dL of total cholesterol, 15 mg/dL of LDL cholesterol, 7 mg/dL of HDL cholesterol, and 29 mg/dL of triglycerides after 48 weeks of use.

Renal Laboratory Tests

In two 48-week trials in antiretroviral treatment-naïve adults with HIV-1 treated with FTC+TAF with EVG+COBI (N=866) with a median baseline eGFR of 115 mL per minute, mean serum creatinine increased by 0.1 mg per dL from baseline to Week 48. Median urine protein-to-creatinine ratio (UPCR) was 44 mg per gram at baseline and at Week 48. In a 48-week trial in virologically-suppressed TDF-treated adults with HIV-1 who switched to FTC+TAF with EVG+COBI (N=959) with a mean baseline eGFR of 112 mL per minute, mean serum creatinine was similar to baseline at Week 48; median UPCR was 61 mg per gram at baseline and 46 mg per gram at Week 48. Across these trials, renal serious adverse events or discontinuations due to renal adverse reactions were encountered in less than 1% of participants treated with FTC+TAF with EVG+COBI.

In a 24-week trial in adults with HIV-1 and renal impairment (baseline eGFR 30 to 69 mL per minute) who received FTC+TAF with EVG+COBI (N=248), mean serum creatinine was 1.5 mg per dL at both baseline and Week 24. Median UPCR was 161 mg per gram at baseline and 93 mg per gram at Week 24. FTC+TAF with EVG+COBI was permanently discontinued due to worsening renal function in two of 80 (3%) participants.

Bone Mineral Density Effects

In the pooled analysis of two 48-week trials of antiretroviral treatment-naïve adult participants with HIV-1, bone mineral density (BMD) from baseline to Week 48 was assessed by dual-energy X-ray absorptiometry (DXA). Mean BMD decreased from baseline to Week 48 −1.30% with FTC+TAF with EVG+COBI at the lumbar spine and −0.66% at the total hip. BMD declines of 5% or greater at the lumbar spine were experienced by 10% of FTC+TAF with EVG+COBI participants. BMD declines of 7% or greater at the femoral neck were experienced by 7% of FTC+TAF with EVG+COBI participants. The long-term clinical significance of these BMD changes is not known.

In 799 virologically-suppressed TDF-treated adult participants with HIV-1 that switched to FTC+TAF with EVG+COBI, at Week 48 mean BMD increased (1.86% lumbar spine, 1.95% total hip). BMD declines of 5% or greater at the lumbar spine were experienced by 1% of FTC+TAF with EVG+COBI participants. BMD declines of 7% or greater at the femoral neck were experienced by 1% of FTC+TAF with EVG+COBI participants.

Adverse Reactions in a Clinical Trial of FTC+TAF with EVG+COBI in Virologically-Suppressed Adults with HIV-1 and End Stage Renal Disease (ESRD) Receiving Chronic Hemodialysis

In a 48-week trial of virologically-suppressed adult participants with HIV-1 and end stage renal disease (ESRD) (estimated creatinine clearance of less than 15 mL/min) on chronic hemodialysis treated with FTC+TAF with EVG+COBI (N=55), the most commonly reported adverse reaction (adverse event assessed as causally related by investigator and all grades) was nausea (7%). Serious adverse events were reported in 53% of participants and the most common serious adverse events were pneumonia (13%), fluid overload (7%), hyperkalemia (7%) and osteomyelitis (7%). Overall 5% of participants permanently discontinued treatment due to an adverse event.

Adverse Reactions in Clinical Trials in Pediatric Participants with HIV-1

Study 106: Adverse Reactions in a Clinical Trial of FTC+TAF with EVG+COBI in Pediatric Participants Weighing at Least 25 kg

The safety profile of FTC+TAF in pediatric participants weighing at least 25 kg is informed by an open-label trial of antiretroviral treatment-naïve pediatric participants with HIV-1 between the ages of 12 to less than 18 years weighing at least 35 kg through 48 weeks (N=50; cohort 1) and virologically-suppressed participants with HIV-1 between the ages of 6 to less than 12 years weighing at least 25 kg (N=52; cohort 2). Participants received FTC+TAF with EVG+COBI through 48 weeks. With the exception of a decrease in the mean CD4+ cell count observed in cohort 2, the safety of this combination was similar to that in adults.

Bone Mineral Density Effects

Cohort 1: Treatment-naïve adolescents (12 to less than 18 years; at least 35 kg)

Among the participants in cohort 1 receiving FTC+TAF with EVG+COBI, mean BMD increased from baseline to Week 48, +4.2% at the lumbar spine and +1.3% for the total body less head (TBLH). Mean changes from baseline BMD Z-scores were −0.07 for lumbar spine and −0.20 for TBLH at Week 48. One participant had significant (at least 4%) lumbar spine BMD loss at Week 48.

Cohort 2: Virologically-suppressed children (6 to less than 12 years; at least 25 kg)

Among the participants in cohort 2 receiving FTC+TAF with EVG+COBI, mean BMD increased from baseline to Week 48, +3.9% at the lumbar spine and +4.2% for TBLH. Mean changes from baseline BMD Z-scores were -0.24 for lumbar spine and -0.19 for TBLH at Week 48. Six participants had significant (at least 4%) lumbar spine BMD loss at Week 48 and 2 participants also had at least 4% TBLH BMD loss at Week 48.

Change from Baseline in CD4+ cell counts

Cohort 2: Virologically-suppressed children (6 to less than 12 years; at least 25 kg)

Cohort 2 evaluated pediatric participants (N=52) who were virologically-suppressed and who switched from their antiretroviral regimen to FTC+TAF with EVG+COBI. Although all participants had HIV-1 RNA < 50 copies/mL, there was a decrease from baseline in CD4+ cell count at Weeks 24 and 48. The mean baseline and mean change from baseline in CD4+ cell count and in CD4% from Week 2 to Week 48 are presented in Table 2. All participants maintained their CD4+ cell counts above 400 cells/mm^3 [see Use in Specific Populations (8.4)].

Table 2 Mean Change in CD4+ Count and CD4 Percentage from Baseline to Week 48 in Virologically-Suppressed Pediatric Participants from 6 to <12 Years Who Switched to FTC+TAF with EVG+COBI
 |  | Mean Change from Baseline
 | Baseline | Week 2 | Week 4 | Week 12 | Week 24 | Week 32 | Week 48
CD4+ Cell Count (cells/mm^3) | 961 (275.5) [Mean (SD)] | -117 | -114 | -112 | -118 | -62 | -66
CD4% | 38 (6.4) | +0.3% | -0.1% | -0.8% | -0.8% | -1.0% | -0.6%

Study 1474: Adverse Reactions in a Clinical Trial of FTC+TAF with Bictegravir in Pediatric Participants Weighing at Least 14 to Less Than 25 kg

In a separate open-label trial of virologically-suppressed participants at least 2 years of age and weighing at least 14 to less than 25 kg (N=22; cohort 3) who received FTC+TAF with bictegravir through 24 weeks, no new adverse reactions or laboratory abnormalities were identified compared to those observed in adults. In this trial, the mean (SD) change from baseline to Week 24 in CD4+ cell count was −126 (264) cells per mm^3 and the mean (SD) change in CD4% from baseline to Week 24 was 0.2% (4.4%).

Study 128: Adverse Reactions in a Clinical Trial of DESCOVY in combination with Darunavir+Cobicistat (DRV+COBI) in Pediatric Participants Weighing at Least 14 kg

The safety profile of DESCOVY is also informed by a separate open-label trial of virologically-suppressed pediatric participants between the ages of 6 to less than 12 years and weighing at least 25 to less than 40 kg (N=9; cohort 2), and virologically-suppressed pediatric participants at least 2 years of age and weighing at least 14 to less than 25 kg (N=11; cohort 3) who received DESCOVY in combination with DRV+COBI through Week 48. In this study, the safety profile of DESCOVY was similar to that in adults.

Bone Mineral Density Effects

Cohort 2: Pediatric Participants Weighing at Least 25 to Less Than 40 kg

Among the participants in cohort 2 who had both baseline and Week 48 measurements (n=8 and 9 for lumbar spine and TBLH, respectively), mean BMD increased from baseline to Week 48, +6.1% at lumbar spine and +4.4% for TBLH.

Cohort 3: Pediatric Participants Weighing at Least 15 to less Than 25 kg

Among the participants in cohort 3 who had both baseline and Week 48 measurements (n=7 and 10 for lumbar spine and TBLH, respectively), mean BMD increased from baseline to Week 48, +8.7% at lumbar spine and +6.9% for TBLH.

Adverse Reactions from Clinical Trial Experience in Individuals without HIV-1 Taking DESCOVY for HIV-1 PrEP

The safety profile of DESCOVY for HIV-1 PrEP was comparable to that observed in clinical trials of participants with HIV based on a double-blind, randomized, active-controlled trial (DISCOVER) in which a total of 5,387 adult men and transgender women without HIV-1 who have sex with men received DESCOVY (N=2,694) or TRUVADA (N=2,693) once daily for HIV-1 PrEP [see Clinical Studies (14.3)]. Median duration of exposure was 86 and 87 weeks, respectively. The most common adverse reaction in participants who received DESCOVY (incidence greater than or equal to 5%, all grades) was diarrhea (5%). Table 3 provides a list of the most common adverse reactions that occurred in 2% or more of participants in either treatment group. The proportion of participants who discontinued treatment with DESCOVY or TRUVADA due to adverse events, regardless of severity, was 1.3% and 1.8%, respectively.

Table 3 Adverse Reactions (All Grades) Reported in ≥2% in Either Arm in the DISCOVER Trial of Participants without HIV-1
 | DESCOVY (N=2,694) | TRUVADA (N=2,693)
Diarrhea | 5% | 6%
Nausea | 4% | 5%
Headache | 2% | 2%
Fatigue | 2% | 3%
Abdominal pain [Includes the following terms: abdominal pain, abdominal pain upper, abdominal pain lower, gastrointestinal pain, and abdominal discomfort] | 2% | 3%

Renal Laboratory Tests

Changes from baseline to Week 48 in renal laboratory data are presented in Table 4. The long-term clinical significance of these renal laboratory changes on adverse reaction frequencies between DESCOVY and TRUVADA is not known.

Table 4 Laboratory Assessments of Renal Function Reported in Participants without HIV-1 Receiving DESCOVY or TRUVADA in the DISCOVER Trial
 | DESCOVY (N=2,694) | TRUVADA (N=2,693)
Serum Creatinine (mg/dL) [Mean (SD).]
Change at Week 48 | −0.01 (0.107) | 0.01 (0.111)
eGFRCG (mL/min) [Median (Q1, Q3).]
Change at Week 48 | 1.8 (−7.2, 11.1) | −2.3 (−10.8, 7.2)
Percentage of Participants who Developed UPCR >200 mg/g [Based on N who had normal UPCR (≤ 200 mg/g) at baseline.]
At Week 48 | 0.7% | 1.5%
eGFRCG=estimated Glomerular Filtration Rate by Cockcroft-Gault; UPCR=urine protein/creatinine ratio

Bone Mineral Density Effects

In the DISCOVER trial, mean increases from baseline to Week 48 of 0.5% at the lumbar spine (N=159) and 0.2% at the total hip (N=158) were observed in participants receiving DESCOVY, compared to mean decreases of 1.1% at the lumbar spine (N=160) and 1.0% at the total hip (N=158) in participants receiving TRUVADA. BMD declines of 5% or greater at the lumbar spine and 7% or greater at the total hip were experienced by 4% and 1% of participants, respectively, in both treatment groups at Week 48. The long-term clinical significance of these BMD changes is not known.

Serum Lipids

Changes from baseline to Week 48 in total cholesterol, HDL-cholesterol, LDL-cholesterol, triglycerides, and total cholesterol to HDL ratio are presented in Table 5.

Table 5 Fasting Lipid Values, Mean Change from Baseline, Reported in Participants without HIV-1 Receiving DESCOVY or TRUVADA in the DISCOVER Trial [Excludes participants who received lipid lowering agents during the treatment period.]
 | DESCOVY (N=2,694) |  | TRUVADA (N=2,693)
 | Baseline | Week 48 | Baseline | Week 48
 | mg/dL | Change [The baseline and change from baseline are for participants with both baseline and Week 48 values.] | mg/dL | Change
Total Cholesterol (fasted) | 176 [N=1,098] | 0 | 176 [N=1,124] | -12
HDL-Cholesterol (fasted) | 51 | -2 | 51 | -5
LDL-Cholesterol (fasted) | 103 [N=1,079] | 0 | 103 [N=1,107] | -7
Triglycerides (fasted) | 109 | +9 | 111 | -1
Total Cholesterol to HDL ratio | 3.7 | 0.2 | 3.7 | 0.1

6.2 Postmarketing Experience

The following adverse reactions have been identified during post-approval use of products containing TAF. Because these reactions are reported voluntarily from a population of uncertain size, it is not always possible to reliably estimate their frequency or establish a causal relationship to drug exposure.

Skin and Subcutaneous Tissue Disorders
Angioedema, urticaria, and rash

Renal and Urinary Disorders
Acute renal failure, acute tubular necrosis, proximal renal tubulopathy, and Fanconi syndrome

7 DRUG INTERACTIONS

7.1 Potential for Other Drugs to Affect One or More Components of DESCOVY

TAF, a component of DESCOVY, is a substrate of P-gp, BCRP, OATP1B1, and OATP1B3. Drugs that strongly affect P-gp and BCRP activity may lead to changes in TAF absorption (see Table 6). Drugs that induce P-gp activity are expected to decrease the absorption of TAF, resulting in decreased plasma concentration of TAF, which may lead to loss of therapeutic effect of DESCOVY and development of resistance. Coadministration of DESCOVY with other drugs that inhibit P-gp and BCRP may increase the absorption and plasma concentration of TAF. TAF is not an inhibitor of CYP1A2, CYP2B6, CYP2C8, CYP2C9, CYP2C19, CYP2D6, or UGT1A1. TAF is a weak inhibitor of CYP3A in vitro. TAF is not an inhibitor or inducer of CYP3A in vivo.

7.2 Drugs Affecting Renal Function

Because FTC and tenofovir are primarily excreted by the kidneys by a combination of glomerular filtration and active tubular secretion, coadministration of DESCOVY with drugs that reduce renal function or compete for active tubular secretion may increase concentrations of FTC, tenofovir, and other renally eliminated drugs and this may increase the risk of adverse reactions. Some examples of drugs that are eliminated by active tubular secretion include, but are not limited to, acyclovir, cidofovir, ganciclovir, valacyclovir, valganciclovir, aminoglycosides (e.g., gentamicin), and high-dose or multiple NSAIDs [see Warnings and Precautions (5.4)].

7.3 Established and Other Potentially Significant Interactions

Table 6 provides a listing of established or potentially clinically significant drug interactions with recommended steps to prevent or manage the drug interaction (the table is not all inclusive). The drug interactions described are based on studies conducted with either DESCOVY, the components of DESCOVY (emtricitabine and tenofovir alafenamide) as individual agents, or are predicted drug interactions that may occur with DESCOVY. For magnitude of interaction, see Clinical Pharmacology (12.3).

Table 6 Established and Other Potentially Significant [This table is not all inclusive.] Drug Interactions
Concomitant Drug Class: Drug Name | Effect on Concentration [↓=Decrease] | Clinical Comment
Antiretroviral Agents: Protease Inhibitors (PI)
tipranavir/ritonavir | ↓ TAF | Coadministration with DESCOVY is not recommended.
atazanavir/cobicistat | ↑ TAF | Coadministration with DESCOVY in pediatric patients weighing 14 to < 35 kg is not recommended [see Use in Specific Populations (8.4)].
Other Agents
Anticonvulsants: carbamazepine oxcarbazepine phenobarbital phenytoin | ↓ TAF | Consider alternative anticonvulsant.
Antimycobacterials: rifabutin rifampin rifapentine | ↓ TAF | Coadministration of DESCOVY with rifabutin, rifampin, or rifapentine is not recommended.
Herbal Products: St. John’s wort (Hypericum perforatum) | ↓ TAF | Coadministration of DESCOVY with St. John’s wort is not recommended.
↑= Increase

7.4 Drugs without Clinically Significant Interactions with DESCOVY

Based on drug interaction studies conducted with the components of DESCOVY, no clinically significant drug interactions have been either observed or are expected when DESCOVY is combined with the following antiretroviral agents: atazanavir with ritonavir, atazanavir with cobicistat (in those weighing ≥35 kg), darunavir with ritonavir or cobicistat, dolutegravir, efavirenz, ledipasvir, lopinavir/ritonavir, maraviroc, nevirapine, raltegravir, rilpivirine, and sofosbuvir.

No clinically significant drug interactions have been either observed or are expected when DESCOVY is combined with the following drugs: buprenorphine, itraconazole, ketoconazole, lorazepam, methadone, midazolam, naloxone, norbuprenorphine, norgestimate/ethinyl estradiol, and sertraline.

8 USE IN SPECIFIC POPULATIONS

8.1 Pregnancy

Pregnancy Exposure Registry

There is a pregnancy exposure registry that monitors pregnancy outcomes in individuals exposed to DESCOVY during pregnancy. Healthcare providers are encouraged to register individuals by calling the Antiretroviral Pregnancy Registry (APR) at 1-800-258-4263.

Risk Summary

Available data from the APR show no statistically significant difference in the overall risk of major birth defects for emtricitabine (FTC) or tenofovir alafenamide (TAF) compared with the background rate for major birth defects of 2.7% in a U.S. reference population of the Metropolitan Atlanta Congenital Defects Program (MACDP) (see Data). The rate of miscarriage for individual drugs is not reported in the APR. The estimated background rate of miscarriage in the clinically recognized pregnancies in the U.S. general population is 15–20%.

In animal studies, no adverse developmental effects were observed when the components of DESCOVY were administered separately during the period of organogenesis at exposures 60 and 108 times (mice and rabbits, respectively) the FTC exposure and at exposure equal to or 53 times (rats and rabbits, respectively) the TAF exposure at the recommended daily dose of DESCOVY (see Data). Likewise, no adverse developmental effects were seen when FTC was administered to mice through lactation at exposures up to approximately 60 times the exposure at the recommended daily dose of DESCOVY. No adverse effects were observed in the offspring when TDF was administered through lactation at tenofovir exposures of approximately 14 times the exposure at the recommended daily dosage of DESCOVY.

Data

Human Data

Prospective reports from the APR of overall major birth defects in pregnancies exposed to the components of DESCOVY are compared with a U.S. background major birth defect rate. Methodological limitations of the APR include the use of MACDP as the external comparator group. The MACDP population is not disease-specific, evaluates women and infants from a limited geographic area, and does not include outcomes for births that occurred at less than 20 weeks gestation.

Emtricitabine (FTC):

Based on prospective reports to the APR of over 7300 exposures to FTC-containing regimens during pregnancy resulting in live births (including over 5400 exposed in the first trimester and over 1800 exposed in the second/third trimester), the prevalence of birth defects in live births was 3.0% (95% CI: 2.5% to 3.5%) and 2.7% (95% CI: 2.0% to 3.6%) following first and second/third trimester exposure, respectively, to FTC-containing regimens.

Tenofovir Alafenamide (TAF):

Based on prospective reports to the APR of over 1600 exposures to TAF-containing regimens during pregnancy resulting in live births (including over 1300 exposed in the first trimester and over 300 exposed in the second/third trimester), the prevalence of birth defects in live births was 3.9% (95% CI: 2.9% to 5.2%) and 4.7% (95% CI: 2.6% to 7.7%) following first and second/third trimester exposure, respectively, to TAF-containing regimens.

Animal Data

Emtricitabine: FTC was administered orally to pregnant mice (250, 500, or 1000 mg/kg/day) and rabbits (100, 300, or 1000 mg/kg/day) through organogenesis (on gestation days 6 through 15, and 7 through 19, respectively). No significant toxicological effects were observed in embryo-fetal toxicity studies performed with FTC in mice at exposures (area under the curve [AUC]) approximately 60 times higher and in rabbits at approximately 108 times higher than human exposures at the recommended daily dose. In a pre/postnatal development study with FTC, mice were administered doses up to 1000 mg/kg/day; no significant adverse effects directly related to drug were observed in the offspring exposed daily from before birth (in utero) through sexual maturity at daily exposures (AUC) of approximately 60-fold higher than human exposures at the recommended daily dose.

Tenofovir Alafenamide: TAF was administered orally to pregnant rats (25, 100, or 250 mg/kg/day) and rabbits (10, 30, or 100 mg/kg/day) through organogenesis (on gestation days 6 through 17, and 7 through 20, respectively). No adverse embryo-fetal effects were observed in rats and rabbits at TAF exposures approximately similar to (rats) and 53 (rabbits) times higher than the exposure in humans at the recommended daily dose of DESCOVY. TAF is rapidly converted to tenofovir; the observed tenofovir exposures in rats and rabbits were 59 (rats) and 93 (rabbits) times higher than human tenofovir exposures at the recommended daily dose. Since TAF is rapidly converted to tenofovir and a lower tenofovir exposure in rats and mice was observed after TAF administration compared to tenofovir disoproxil fumarate (TDF, another prodrug for tenofovir) administration, a pre/postnatal development study in rats was conducted only with TDF. Doses up to 600 mg/kg/day were administered through lactation; no adverse effects were observed in the offspring on gestation day 7 (and lactation day 20) at tenofovir exposures of approximately 14 (21) times higher than the exposures in humans at the recommended daily dose of DESCOVY.

8.2 Lactation

Risk Summary

Data from the published literature report the presence of FTC, TAF, and tenofovir in human milk. Data from the published literature have not reported adverse effects of FTC or TAF on a breastfed child. There are no data on the effects of FTC or TAF on milk production.

Potential risks of breastfeeding include: 1) HIV transmission to infants without HIV-1; 2) developing viral resistance in infants with HIV-1; and 3) adverse reactions in a breastfed infant similar to those seen in adults.

8.4 Pediatric Use

The safety and effectiveness of DESCOVY for the treatment of HIV-1 infection have been established in pediatric patients weighing at least 14 kg [see Indications and Usage (1.1) and Dosage and Administration (2.2)].

Treatment of HIV-1 Infection

Adolescent Patients Weighing at Least 35 kg:

The safety and effectiveness of DESCOVY in combination with other antiretroviral agents for the treatment of HIV-1 infection was established in adolescent patients weighing at least 35 kg.

Use of DESCOVY in adolescent patients is supported by adequate and well controlled trials of FTC+TAF with EVG+COBI in adults and by an open-label trial in antiretroviral treatment-naïve pediatric participants with HIV-1 aged 12 to less than 18 years and weighing at least 35 kg through Week 48 (N=50; Study 106 [cohort 1]) administered FTC+TAF with EVG+COBI. The safety and effectiveness of FTC+TAF with EVG+COBI in adolescent participants was similar to that in adults on this regimen [see Adverse Reactions (6.1), Clinical Pharmacology (12.3), and Clinical Studies (14.2)].

Pediatric Patients Weighing at least 14 kg and Less than 35 kg:

The safety and effectiveness of DESCOVY in combination with other antiretroviral agents, including darunavir and cobicistat (DRV+COBI) but not including other protease inhibitors that require a CYP3A inhibitor, for the treatment of HIV-1 infection was established in pediatric patients weighing at least 14 kg to less than 35 kg [see Adverse Reactions (6.1), Clinical Pharmacology (12.3), and Clinical Studies (14.2)].

Use of DESCOVY in pediatric patients weighing at least 14 kg to less than 35 kg is supported by:

- adequate and well controlled trials of FTC+TAF with EVG+COBI in adults;
- an open-label trial in virologically-suppressed pediatric participants aged 6 to less than 12 years and weighing at least 25 kg (N=52; Study 106 [cohort 2]) administered FTC+TAF with EVG+COBI through Week 48;
- an open-label trial of DESCOVY administered in combination with DRV+COBI in virologically-suppressed pediatric participants at least 2 years of age and weighing at least 14 kg to less than 40 kg (n=20; Study 128 [cohort 2 and 3]) through Week 48;
- an open-label trial of FTC+TAF with bictegravir in virologically-suppressed pediatric participants at least 2 years of age and weighing at least 14 to less than 25 kg through Week 24 (N=22; Study 1474 [cohort 3]).
  Overall, the safety and effectiveness of FTC+TAF in pediatric participants in these trials were similar to that observed in adults. Specifically, the safety and efficacy of FTC+TAF with EVG+COBI in participants 6 to 12 years of age and weighing at least 25 kg were similar to that in antiretroviral treatment-naïve adults and adolescents receiving this regimen, with the exception of a decrease from baseline in CD4+ cell count. The safety and effectiveness of DESCOVY when administered with DRV+COBI in pediatric participants weighing at least 14 kg to less than 40 kg were similar to that in adults.

Use of DESCOVY with Other Protease Inhibitors that Require CYP3A Inhibition in Pediatric Patients Weighing at least 14 kg to Less than 35 kg:

The use of DESCOVY with atazanavir and cobicistat (ATV+COBI) is not recommended in pediatric patients weighing at least 14 kg to less than 35 kg.

The use of DESCOVY with ATV+COBI was studied in pediatric patients weighing at least 14 kg to less than 35 kg. In Study 128, participants who received ATV+COBI in cohort 2 (25 kg to <40 kg, n=14) and cohort 3 (14 kg to <25 kg, n=15) showed TAF exposures (Cmax and AUC) that exceeded adult exposures by 4–5-fold in cohort 2, and 2–3-fold in cohort 3. Limited safety data were available to support the increased TAF exposures. Therefore, the use of DESCOVY with ATV+COBI is not recommended in pediatric patients weighing at least 14 kg to less than 35 kg.

Safety and effectiveness of DESCOVY in combination with protease inhibitors that require ritonavir in pediatric patients weighing at least 14 kg to less than 35 kg have not been established.

Pediatric Patients Weighing less than 14 kg:

Safety and effectiveness of DESCOVY for treatment of HIV-1 infection in pediatric patients weighing less than 14 kg have not been established.

HIV-1 PrEP

Safety and effectiveness of DESCOVY for HIV-1 PrEP in at-risk adolescents weighing at least 35 kg, excluding individuals at risk from receptive vaginal sex, is supported by data from an adequate and well-controlled trial of DESCOVY for HIV-1 PrEP in adults with additional data from safety and pharmacokinetic studies in previously conducted trials with the individual drug products, FTC and TAF, with EVG+COBI, in adults and pediatric participants with HIV-1 [see Dosage and Administration (2.5), Adverse Reactions (6.1), Clinical Pharmacology (12.3 and 12.4), and Clinical Studies (14)].

While using DESCOVY for HIV-1 PrEP, HIV-1 testing should be repeated at least every 3 months, and upon diagnosis of any other STIs. Previous studies in at-risk adolescents indicated waning adherence to a daily oral PrEP regimen once visits were switched from monthly to quarterly visits. Adolescents may therefore benefit from more frequent visits and counseling [see Warnings and Precautions (5.2)].

Safety and effectiveness of DESCOVY for HIV-1 PrEP in pediatric individuals weighing less than 35 kg have not been established.

8.5 Geriatric Use

In clinical trials of an FTC+TAF-containing regimen for treatment of HIV-1, 80 of the 97 participants enrolled aged 65 years and over received FTC+TAF and EVG+COBI. No differences in safety or efficacy have been observed between elderly participants and adults between 18 and less than 65 years of age.

8.6 Renal Impairment

No dosage adjustment of DESCOVY is recommended in individuals with estimated creatinine clearance greater than or equal to 30 mL per minute, or in adults with ESRD (estimated creatinine clearance below 15 mL per minute) who are receiving chronic hemodialysis. On days of hemodialysis, administer the daily dose of DESCOVY after completion of hemodialysis treatment.

Safety and effectiveness of DESCOVY coadministered with an HIV-1 protease inhibitor that is administered with either ritonavir or cobicistat have not been established in patients with ESRD [see Dosage and Administration (2.3)].

DESCOVY is not recommended in individuals with severe renal impairment (estimated creatinine clearance of 15 to below 30 mL per minute), or in individuals with ESRD who are not receiving chronic hemodialysis, as the safety of DESCOVY has not been established in these populations [see Dosage and Administration (2.6) and Clinical Studies (14.2)].

8.7 Hepatic Impairment

No dosage adjustment of DESCOVY is recommended in individuals with mild (Child-Pugh Class A) or moderate (Child-Pugh Class B) hepatic impairment. DESCOVY has not been studied in individuals with severe hepatic impairment (Child-Pugh Class C) [see Clinical Pharmacology (12.3)].

10 OVERDOSAGE

No data are available on overdose of DESCOVY in patients. If overdose occurs, monitor the individual for evidence of toxicity. Treatment of overdose with DESCOVY consists of general supportive measures including monitoring of vital signs as well as observation of the clinical status of the individual.

Emtricitabine (FTC): Limited clinical experience is available at doses higher than the recommended dose of FTC in DESCOVY. In one clinical pharmacology study, single doses of FTC 1200 mg (6 times the FTC dose in DESCOVY) were administered to 11 participants. No severe adverse reactions were reported. The effects of higher doses are not known.

Hemodialysis treatment removes approximately 30% of the FTC dose over a 3-hour dialysis period starting within 1.5 hours of FTC dosing (blood flow rate of 400 mL per minute and a dialysate flow rate of 600 mL per minute). It is not known whether FTC can be removed by peritoneal dialysis.

Tenofovir Alafenamide (TAF): Limited clinical experience is available at doses higher than the recommended dose of TAF. A single dose of 125 mg TAF (5 times the TAF dose in 200/25 mg DESCOVY) was administered to 48 healthy participants; no serious adverse reactions were reported. The effects of higher doses are unknown. Tenofovir is efficiently removed by hemodialysis with an extraction coefficient of approximately 54%.

11 DESCRIPTION

DESCOVY (emtricitabine and tenofovir alafenamide) is a fixed dose combination tablet containing emtricitabine (FTC) and tenofovir alafenamide (TAF) for oral administration.

- FTC, a synthetic nucleoside analog of cytidine, is an HIV nucleoside analog reverse transcriptase inhibitor (HIV NRTI).
- TAF, an HIV NRTI, is converted in vivo to tenofovir, an acyclic nucleoside phosphonate (nucleotide) analog of adenosine 5′-monophosphate.

DESCOVY tablets are available in two dose strengths:

- 200 mg/25 mg tablets: 200 mg of FTC and 25 mg of TAF (equivalent to 28 mg of tenofovir alafenamide fumarate).
- 120 mg/15 mg tablets: 120 mg of FTC and 15 mg of TAF (equivalent to 16.8 mg of tenofovir alafenamide fumarate).

Both dose strengths of DESCOVY tablets include the following inactive ingredients: croscarmellose sodium, magnesium stearate, and microcrystalline cellulose. The 200 mg/ 25 mg tablets are film-coated with a coating material containing indigo carmine aluminum lake, polyethylene glycol, polyvinyl alcohol, talc, and titanium dioxide. The 120 mg/15 mg tablets are film-coated with a coating material containing polyvinyl alcohol, titanium dioxide, polyethylene glycol, and talc.

Emtricitabine: The chemical name of FTC is 4-amino-5-fluoro-1-(2R-hydroxymethyl-1,3-oxathiolan-5S-yl)-(1H)-pyrimidin-2-one. FTC is the (-)enantiomer of a thio analog of cytidine, which differs from other cytidine analogs in that it has a fluorine in the 5 position.

FTC has a molecular formula of C8H10FN3O3S and a molecular weight of 247.24 and has the following structural formula:

FTC is a white to off-white powder with a solubility of approximately 112 mg per mL in water at 25 °C.

Tenofovir Alafenamide: The chemical name of tenofovir alafenamide fumarate drug substance is L-alanine, N-[(S)-[[(1R)-2-(6-amino-9H-purin-9-yl)-1-methylethoxy]methyl]phenoxyphosphinyl]-, 1-methylethyl ester, (2E)-2-butenedioate (2:1).

Tenofovir alafenamide fumarate has an empirical formula of C21H29O5N6P•½(C4H4O4) and a formula weight of 534.50 and has the following structural formula:

Tenofovir alafenamide fumarate is a white to off-white or tan powder with a solubility of 4.7 mg per mL in water at 20 °C.

12 CLINICAL PHARMACOLOGY

12.1 Mechanism of Action

DESCOVY is a fixed dose combination of antiretroviral drugs emtricitabine (FTC) and tenofovir alafenamide (TAF) [see Microbiology (12.4)].

12.2 Pharmacodynamics

Cardiac Electrophysiology

In a thorough QT/QTc study in 48 healthy participants, TAF at the recommended dose or at a dose approximately 5 times the recommended dose, did not affect the QT/QTc interval and did not prolong the PR interval. The effect of the other component of DESCOVY, FTC, or the combination of FTC and TAF on the QT interval is not known.

12.3 Pharmacokinetics

Absorption, Distribution, Metabolism, and Excretion

The pharmacokinetic (PK) properties of the components of DESCOVY are provided in Table 7. The multiple dose PK parameters of FTC and TAF and its metabolite tenofovir are provided in Table 8. HIV status has no effect on the pharmacokinetics of FTC and TAF in adults.

Table 7 Pharmacokinetic Properties of the Components of DESCOVY
 | Emtricitabine | Tenofovir Alafenamide
Absorption
Tmax (h) | 3 | 1
Effect of high fat meal (relative to fasting) [Values refer to geometric mean ratio [High-fat meal/ fasting] in PK parameters and (90% confidence interval). High-calorie/high-fat meal = ~800 kcal, 50% fat.] | AUC Ratio = 0.91 (0.89, 0.93) Cmax Ratio = 0.74 (0.69, 0.78) | AUC Ratio = 1.75 (1.64, 1.88) Cmax Ratio= 0.85 (0.75, 0.95)
Distribution
% Bound to human plasma proteins | <4 | ~80
Source of protein binding data | In vitro | Ex vivo
Blood-to-plasma ratio | 0.6 | 1.0
Metabolism
Metabolism | Not significantly metabolized | Cathepsin A [In vivo, TAF is hydrolyzed within cells to form tenofovir (major metabolite), which is phosphorylated to the active metabolite, tenofovir diphosphate. In vitro studies have shown that TAF is metabolized to tenofovir by cathepsin A in PBMCs and macrophages; and by CES1 in hepatocytes. Upon coadministration with the moderate CYP3A inducer probe efavirenz, TAF exposure was unaffected.] (PBMCs) CES1 (hepatocytes) CYP3A (minimal)
Elimination
Major route of elimination | Glomerular filtration and active tubular secretion | Metabolism (>80% of oral dose)
t1/2 (h) [t1/2 values refer to median terminal plasma half-life. Note that the pharmacologically active metabolite, tenofovir diphosphate, has a half-life of 150-180 hours within PBMCs.] | 10 | 0.51
% Of dose excreted in urine [Dosing in mass balance studies: FTC (single dose administration of [^14C] emtricitabine after multiple dosing of emtricitabine for 10 days); TAF (single dose administration of [^14C] tenofovir alafenamide).] | 70 | <1
% Of dose excreted in feces | 13.7 | 31.7
PBMCs=peripheral blood mononuclear cells; CES1=carboxylesterase 1

Table 8 Multiple Dose PK Parameters of Emtricitabine, Tenofovir Alafenamide and its Metabolite Tenofovir Following Oral Administration with Food in Adults with HIV-1
Parameter Mean (CV%) | Emtricitabine [From Intensive PK analysis in a phase 2 trial in adults with HIV-1 treated with FTC+TAF and EVG+COBI.] | Tenofovir Alafenamide [From Population PK analysis in two trials of treatment-naïve adults with HIV-1 treated with FTC+TAF with EVG+COBI (N=539).] | Tenofovir [From Population PK analysis in two trials of treatment-naïve adults with HIV-1 treated with FTC+TAF with EVG+COBI (N=841).]
Cmax (microgram per mL) | 2.1 (20.2) | 0.16 (51.1) | 0.02 (26.1)
AUCtau (microgram•hour per mL) | 11.7 (16.6) | 0.21 (71.8) | 0.29 (27.4)
Ctrough (microgram per mL) | 0.10 (46.7) | NA | 0.01 (28.5)
CV=Coefficient of Variation; NA=Not Applicable

Specific Populations

Geriatric Patients

Pharmacokinetics of FTC and TAF have not been fully evaluated in the elderly (65 years of age and older). Population pharmacokinetics analysis of participants with HIV in Phase 2 and Phase 3 trials of FTC+TAF and EVG+COBI showed that age did not have a clinically relevant effect on exposures of TAF up to 75 years of age [see Use in Specific Populations (8.5)].

Pediatric Patients

Treatment of HIV-1 Infection: Mean exposures of TAF in 24 pediatric participants with HIV-1 aged 12 to less than 18 years who received FTC+TAF with EVG+COBI were decreased (23% for AUC) and FTC exposures were similar compared to exposures achieved in treatment-naïve adults following administration of this dosage regimen. The TAF exposure differences are not thought to be clinically significant based on exposure-response relationships (Table 9).

Table 9 Multiple Dose PK Parameters of Emtricitabine, Tenofovir Alafenamide, and its Metabolite Tenofovir Following Oral Administration of FTC+TAF with EVG+COBI in Pediatric Participants with HIV-1 Aged 12 to less than 18 Years [From Intensive PK analysis in a trial in treatment-naïve pediatric participants with HIV-1 infection (N=24).]
Parameter Mean (CV%) | Emtricitabine | Tenofovir Alafenamide | Tenofovir
Cmax (microgram per mL) | 2.3 (22.5) | 0.17 (64.4) | 0.02 (23.7)
AUCtau (microgram•hour per mL) | 14.4 (23.9) | 0.20 [N=23] (50.0) | 0.29 (18.8)
Ctrough (microgram per mL) | 0.10 (38.9) | NA | 0.01 (21.4)
CV = Coefficient of Variation; NA = Not Applicable

Exposures of FTC and TAF achieved in 23 pediatric participants with HIV-1 between the ages of 6 to less than 12 years and weighing at least 25 kg (55 lbs) who received FTC+TAF with EVG+COBI were higher (20% to 80% for AUC) than exposures achieved in adults receiving this same dosage regimen; the increases were not considered clinically significant (Table 10) [see Use in Specific Populations (8.4)].

Table 10 Multiple Dose PK Parameters of Emtricitabine, Tenofovir Alafenamide and its Metabolite Tenofovir Following Oral Administration of FTC+TAF with EVG+COBI in Pediatric Participants with HIV-1 Aged 6 to less than 12 Years [From Intensive PK analysis in a trial in virologically-suppressed pediatric participants with HIV-1 (N=23).]
Parameter Mean (CV%) | Emtricitabine | Tenofovir Alafenamide | Tenofovir
Cmax (microgram per mL) | 3.4 (27.0) | 0.31 (61.2) | 0.03 (20.8)
AUCtau (microgram•hour per mL) | 20.6 [N=22] (18.9) | 0.33 (44.8) | 0.44 (20.9)
Ctrough (microgram per mL) | 0.11 (24.1) | NA | 0.02 (24.9)
CV = Coefficient of Variation; NA = Not Applicable

Exposures of FTC and TAF (AUCtau and Cmax) achieved in 22 pediatric participants with HIV-1 at least 2 years of age and weighing from 14 to less than 25 kg who received FTC+TAF with bictegravir were higher than exposures in adults; the increases were not considered clinically significant as the safety profiles were similar in adult and pediatric patients (Table 11) [see Use in Specific Populations (8.4)].

Table 11 Multiple Dose Pharmacokinetic Parameters of Emtricitabine and Tenofovir Alafenamide Following Oral Administration of FTC+TAF with Bictegravir in Pediatric Participants with HIV-1 at least 2 Years of Age and Weighing from 14 to Less than 25 kg [This trial enrolled virologically-suppressed pediatric participants with HIV-1 from 3 to 9 years of age.]
Parameter Mean (CV%) | Emtricitabine [From Intensive PK analysis (n=12 except n=11 for Ctrough for FTC).] | Tenofovir Alafenamide
Cmax (microgram per mL) | 3.85 (34.7) | 0.414 (31.0)
AUCtau (microgram•h per mL) | 15.0 (21.9) | 0.305 (42.6)
Ctrough (microgram per mL) | 0.210 (243) | NA
CV = Coefficient of Variation; NA = Not Applicable

Exposures of FTC and TAF (AUCtau and Cmax) achieved in 9 pediatric participants with HIV-1 between the ages of 6 to less than 12 years and weighing at least 25 kg to less than 40 kg who received DESCOVY in combination with DRV+COBI were generally higher than exposures achieved in adults; however, the increases were not considered clinically significant (Table 12).

Table 12 Multiple Dose Pharmacokinetic Parameters of Emtricitabine, Tenofovir Alafenamide and its Metabolite Tenofovir Following Oral Administration of DESCOVY with DRV+COBI in Pediatric Participants with HIV-1 Aged 6 to less than 12 Years and Weighing from 25 to less than 40 kg [From Intensive PK analysis in a trial of pediatric participants (n=9)]
Parameter Mean (CV%) | Emtricitabine | Tenofovir Alafenamide | Tenofovir
Cmax (microgram per mL) | 4.17 (25.9) | 0.27 [n=8] (58.1) | 0.06 (12.9)
AUCtau (microgram•h per mL) | 29.4 (35.7) | 0.53 [n=6] (82.9) | 1.11 (15.8)
Ctrough (microgram per mL) | 0.17 (39.4) | NA | 0.04 (19.3)
CV = Coefficient of Variation; NA = Not Applicable

Exposures of FTC and TAF (AUCtau and Cmax) achieved in 11 pediatric participants with HIV-1 at least 2 years of age and weighing at least 14 to less than 25 kg who received DESCOVY in combination with DRV+COBI were generally higher than exposures achieved in adults; however, the increases were not considered clinically significant (Table 13).

Table 13 Multiple Dose Pharmacokinetic Parameters of Emtricitabine, Tenofovir Alafenamide and its Metabolite Tenofovir Following Oral Administration of DESCOVY with DRV+COBI in Pediatric Participants with HIV-1 at least 2 Years of Age and Weighing from 14 kg to less than 25 kg [From Intensive PK analysis in a trial of pediatric participants (n=11)]
Parameter Mean (CV%) | Emtricitabine | Tenofovir Alafenamide | Tenofovir
Cmax (microgram per mL) | 4.40 (16.5) | 0.48 [n=10] (38.8) | 0.06 (36.7)
AUCtau (microgram•h per mL) | 22.9 (13.8) | 0.43 [n=9] (75.9) | 1.05 (38.8)
Ctrough (microgram per mL) | 0.10 (36.7) | NA | 0.03 (36.6)
CV = Coefficient of Variation; NA = Not Applicable

HIV-1 PrEP: The pharmacokinetic data for FTC and TAF following administration of DESCOVY in adolescents without HIV-1 weighing 35 kg and above are not available. The dosage recommendations of DESCOVY for HIV-1 PrEP in this population are based on known pharmacokinetic information in adolescents with HIV-1 taking FTC and TAF for treatment [see Use in Specific Populations (8.4)].

Race and Gender

Based on population pharmacokinetic analyses, there are no clinically meaningful differences based on race or gender.

Patients with Renal Impairment

The pharmacokinetics of FTC+TAF combined with EVG+COBI in participants with HIV-1 and renal impairment (eGFR 30 to 69 mL per minute by Cockcroft-Gault method), and in participants with HIV-1 and ESRD (eGFR less than 15 mL per minute by Cockcroft-Gault method) receiving chronic hemodialysis were evaluated in subsets of virologically-suppressed participants in open-label trials. The pharmacokinetics of TAF were similar among healthy participants, participants with HIV-1 and mild or moderate renal impairment, and participants with HIV-1 and ESRD receiving chronic hemodialysis; increases in FTC and TFV exposures in participants with HIV-1 and renal impairment were not considered clinically relevant (Table 14).

Table 14 Pharmacokinetics of the Components of DESCOVY and a Metabolite of TAF (Tenofovir) in Adults with HIV-1 and Renal Impairment Compared to Participants with HIV-1 and Normal Renal Function
 | AUCtau (microgram∙hour per mL) Mean (CV%)
Estimated Creatinine Clearance [By Cockcroft-Gault method.] | ≥90 mL per minute (N=18) [From a phase 2 trial in adults with HIV-1 and normal renal function treated with FTC+TAF with EVG+COBI.] | 60–89 mL per minute (N=11) [These participants had an eGFR ranging from 60 to 69 mL per minute.] | 30–59 mL per minute (N=18) [From a phase 3 trial in adults with HIV-1 and renal impairment treated with FTC+TAF with EVG+COBI.] | <15 mL per minute (N=12) [From a phase 3 trial in adults with HIV-1 and ESRD receiving chronic hemodialysis treated with FTC+TAF with EVG+COBI; PK assessed prior to hemodialysis following 3 consecutive daily doses of FTC+TAF with EVG+COBI.]
Emtricitabine | 11.4 (11.9) | 17.6 (18.2) | 23.0 (23.6) | 62.9 (48.0) [N = 11.]
Tenofovir | 0.32 (14.9) | 0.46 (31.5) | 0.61 (28.4) | 8.72 (39.4) [N = 10.]

Patients with Hepatic Impairment

Emtricitabine: The pharmacokinetics of FTC has not been studied in participants with hepatic impairment; however, FTC is not significantly metabolized by liver enzymes, so the impact of hepatic impairment should be limited.

Tenofovir Alafenamide: Clinically relevant changes in tenofovir pharmacokinetics in participants with hepatic impairment were not observed in participants with mild to moderate (Child-Pugh Class A and B) hepatic impairment [see Use in Specific Populations (8.7)].

Hepatitis B and/or Hepatitis C Virus Infection

The pharmacokinetics of FTC and TAF have not been fully evaluated in participants with hepatitis B and/or C virus.

Drug Interaction Studies

The effects of coadministered drugs on the exposure of TAF are shown in Table 15 and the effects of DESCOVY or its components on the exposure of coadministered drugs are shown in Table 16 [these studies were conducted with DESCOVY or the components of DESCOVY (FTC or TAF) administered alone]. For information regarding clinical recommendations, see Drug Interactions (7).

Table 15 Drug Interactions: Changes in TAF Pharmacokinetic Parameters in the Presence of Coadministered Drug(s) [All interaction studies conducted in healthy participants.]
Coadministered Drug | Coadministered Drug(s) Dosage (once daily) (mg) | Tenofovir Alafenamide Dosage (once daily) (mg) | N | Mean Ratio of TAF PK Parameters (90% CI); No effect = 1.00
Coadministered Drug | Coadministered Drug(s) Dosage (once daily) (mg) | Tenofovir Alafenamide Dosage (once daily) (mg) | N | Cmax | AUC | Cmin
Atazanavir | 300 (+100 ritonavir) | 10 | 10 | 1.77 (1.28, 2.44) | 1.91 (1.55, 2.35) | NC
Cobicistat | 150 | 8 | 12 | 2.83 (2.20, 3.65) | 2.65 (2.29, 3.07) | NC
Darunavir | 800 (+150 cobicistat) | 25 [Study conducted with DESCOVY (FTC/TAF).] | 11 | 0.93 (0.72, 1.21) | 0.98 (0.80, 1.19) | NC
Darunavir | 800 (+100 ritonavir) | 10 | 10 | 1.42 (0.96, 2.09) | 1.06 (0.84, 1.35) | NC
Dolutegravir | 50 | 10 | 10 | 1.24 (0.88, 1.74) | 1.19 (0.96, 1.48) | NC
Efavirenz | 600 | 40 | 11 | 0.78 (0.58, 1.05) | 0.86 (0.72, 1.02) | NC
Lopinavir | 800 (+200 ritonavir) | 10 | 10 | 2.19 (1.72, 2.79) | 1.47 (1.17, 1.85) | NC
Rilpivirine | 25 | 25 | 17 | 1.01 (0.84, 1.22) | 1.01 (0.94, 1.09) | NC
Sertraline | 50 (dosed as a single dose) | 10 [Study conducted with FTC+TAF with EVG+COBI.] | 19 | 1.00 (0.86, 1.16) | 0.96 (0.89, 1.03) | NC
NC=Not Calculated

Table 16 Drug Interactions: Changes in PK Parameters for Coadministered Drug in the Presence of DESCOVY or the Individual Components [All interaction studies conducted in healthy participants.]
Coadministered Drug | Coadministered Drug Dosage (once daily) (mg) | Tenofovir Alafenamide Dosage (once daily) (mg) | N | Mean Ratio of Coadministered Drug PK Parameters (90% CI); No effect = 1.00
Coadministered Drug | Coadministered Drug Dosage (once daily) (mg) | Tenofovir Alafenamide Dosage (once daily) (mg) | N | Cmax | AUC | Cmin
Atazanavir | 300 +100 ritonavir | 10 | 10 | 0.98 (0.89, 1.07) | 0.99 (0.96, 1.01) | 1.00 (0.96, 1.04)
Darunavir | 800 +150 cobicistat | 25 [Study conducted with DESCOVY (FTC/TAF).] | 11 | 1.02 (0.96, 1.09) | 0.99 (0.92, 1.07) | 0.97 (0.82, 1.15)
Darunavir | 800 +100 ritonavir | 10 | 10 | 0.99 (0.91, 1.08) | 1.01 (0.96, 1.06) | 1.13 (0.95, 1.34)
Dolutegravir | 50 mg | 10 | 10 | 1.15 (1.04, 1.27) | 1.02 (0.97, 1.08) | 1.05 (0.97, 1.13)
Lopinavir | 800 +200 ritonavir | 10 | 10 | 1.00 (0.95, 1.06) | 1.00 (0.92, 1.09) | 0.98 (0.85, 1.12)
Midazolam [A sensitive CYP3A4 substrate.] | 2.5 (single dose, orally) | 25 | 18 | 1.02 (0.92, 1.13) | 1.13 (1.04, 1.23) | NC
Midazolam [A sensitive CYP3A4 substrate.] | 1 (single dose, intravenous) | 25 | 18 | 0.99 (0.89, 1.11) | 1.08 (1.04, 1.14) | NC
Rilpivirine | 25 | 25 | 16 | 0.93 (0.87, 0.99) | 1.01 (0.96, 1.06) | 1.13 (1.04, 1.23)
Sertraline | 50 (single dose) | 10 [Study conducted with FTC+TAF with EVG+COBI.] | 19 | 1.14 (0.94, 1.38) | 0.93 (0.77, 1.13) | NC
NC=Not Calculated

12.4 Microbiology

Mechanism of Action

Emtricitabine: FTC, a synthetic nucleoside analog of cytidine, is phosphorylated by cellular enzymes to form emtricitabine 5'-triphosphate. Emtricitabine 5'-triphosphate inhibits the activity of the HIV-1 reverse transcriptase by competing with the natural substrate deoxycytidine 5'-triphosphate and by being incorporated into nascent viral DNA which results in chain termination. Emtricitabine 5′-triphosphate is a weak inhibitor of mammalian DNA polymerases α, β, Ɛ, and mitochondrial DNA polymerase γ.

Tenofovir Alafenamide: TAF is a phosphonoamidate prodrug of tenofovir (2’-deoxyadenosine monophosphate analog). Plasma exposure to TAF allows for permeation into cells and then TAF is intracellularly converted to tenofovir through hydrolysis by cathepsin A. Tenofovir is subsequently phosphorylated by cellular kinases to the active metabolite tenofovir diphosphate. Tenofovir diphosphate inhibits HIV-1 replication through incorporation into viral DNA by the HIV reverse transcriptase, which results in DNA chain-termination.

Tenofovir has activity against HIV-1. Cell culture studies have shown that both tenofovir and FTC can be fully phosphorylated when combined in cells. Tenofovir diphosphate is a weak inhibitor of mammalian DNA polymerases that include mitochondrial DNA polymerase γ and there is no evidence of toxicity to mitochondria in cell culture.

Antiviral Activity in Cell Culture

Emtricitabine: The antiviral activity of FTC against laboratory and clinical isolates of HIV-1 was assessed in T lymphoblastoid cell lines, the MAGI-CCR5 cell line, and primary peripheral blood mononuclear cells. The EC50 values for FTC were in the range of 1.3–640 nM. FTC displayed antiviral activity in cell culture against HIV-1 clades A, B, C, D, E, F, and G (EC50 values ranged from 7-75 nM) and showed strain specific activity against HIV-2 (EC50 values ranged from 7–1,500 nM).

In a study of FTC with a broad panel of representatives from the major classes of approved anti-HIV agents (NRTIs, non-nucleoside reverse transcriptase inhibitors [NNRTIs], integrase strand transfer inhibitors [INSTIs], and PIs) no antagonism was observed for these combinations.

Tenofovir Alafenamide: The antiviral activity of TAF against laboratory and clinical isolates of HIV-1 subtype B was assessed in lymphoblastoid cell lines, PBMCs, primary monocyte/macrophage cells and CD4^+-T lymphocytes. The EC50 values for TAF ranged from 2.0 to 14.7 nM.

TAF displayed antiviral activity in cell culture against all HIV-1 groups (M, N, O), including sub-types A, B, C, D, E, F, and G (EC50 values ranged from 0.10 to 12.0 nM) and strain specific activity against HIV-2 (EC50 values ranged from 0.91 to 2.63 nM).

In a study of TAF with a broad panel of representatives from the major classes of approved anti-HIV agents (NRTIs, NNRTIs, INSTIs, and PIs) no antagonism was observed for these combinations.

Prophylactic Activity in a Nonhuman Primate Model of HIV-1 Transmission

Emtricitabine and Tenofovir Alafenamide: The prophylactic activity of the combination of oral FTC and TAF was evaluated in a controlled study of macaques administered once weekly intra-rectal inoculations of chimeric simian/human immunodeficiency type 1 virus (SHIV) for up to 19 weeks (n=6). All 6 macaques that received FTC and TAF at doses resulting in PBMC exposures consistent with those achieved in humans administered a dose of FTC/TAF 200/25 mg remained SHIV uninfected.

Resistance

In Cell Culture

Emtricitabine: HIV-1 isolates with reduced susceptibility to FTC were selected in cell culture and in participants treated with FTC. Reduced susceptibility to FTC was associated with M184V or I substitutions in HIV-1 RT.

Tenofovir Alafenamide: HIV-1 isolates with reduced susceptibility to TAF were selected in cell culture. HIV-1 isolates selected by TAF expressed a K65R substitution in HIV-1 RT, sometimes in the presence of S68N or L429I substitutions; in addition, a K70E substitution in HIV-1 RT was observed.

In Clinical Trials

Treatment of HIV-1

The resistance profile of DESCOVY in combination with other antiretroviral agents for the treatment of HIV-1 infection is based on studies of FTC+TAF with EVG+COBI in the treatment of HIV-1 infection. In a pooled analysis of antiretroviral-naïve participants, genotyping was performed on plasma HIV-1 isolates from all participants with HIV-1 RNA greater than 400 copies per mL at confirmed virologic failure, at Week 48, or at time of early study drug discontinuation. Genotypic resistance developed in 7 of 14 evaluable participants. The resistance-associated substitutions that emerged were M184V/I (N=7) and K65R (N=1). Three participants had virus with emergent R, H, or E at the polymorphic Q207 residue in reverse transcriptase.

One participant was identified with emergent resistance to FTC (M184M/I) out of 4 virologic failure participants in a clinical study of virologically-suppressed participants who switched from a regimen containing FTC+TDF to FTC+TAF with EVG+COBI (N=799).

HIV-1 PrEP

In the DISCOVER trial of HIV-1 uninfected men and transgender women who have sex with men and who are at risk of HIV-1 infection receiving DESCOVY or TRUVADA for HIV-1 PrEP, genotyping was performed on participants found to be infected during the trial who had HIV-1 RNA ≥400 copies/mL (6 of 7 participants receiving DESCOVY and 13 of 15 participants receiving TRUVADA). The development of FTC resistance-associated substitutions, M184I and/or M184V, was observed in 4 HIV-1 infected participants in the TRUVADA group who had suspected baseline infections.

Cross-Resistance

Emtricitabine: FTC-resistant viruses with the M184V or I substitution were cross-resistant to lamivudine, but retained sensitivity to didanosine, stavudine, tenofovir, and zidovudine.

Viruses harboring substitutions conferring reduced susceptibility to stavudine and zidovudine-thymidine analog substitutions (M41L, D67N, K70R, L210W, T215Y/F, K219Q/E) or didanosine (L74V) remained sensitive to FTC. HIV-1 containing the K103N substitution or other substitutions associated with resistance to NNRTIs was susceptible to FTC.

Tenofovir Alafenamide: Tenofovir resistance substitutions K65R and K70E result in reduced susceptibility to abacavir, didanosine, emtricitabine, lamivudine, and tenofovir.

HIV-1 with multiple thymidine analog substitutions (M41L, D67N, K70R, L210W, T215F/Y, K219Q/E/N/R), or multinucleoside resistant HIV-1 with a T69S double insertion mutation or with a Q151M substitution complex including K65R, showed reduced susceptibility to TAF in cell culture.

13 NONCLINICAL TOXICOLOGY

13.1 Carcinogenesis, Mutagenesis, Impairment of Fertility

Emtricitabine

In long-term carcinogenicity studies of FTC, no drug-related increases in tumor incidence were found in mice at doses up to 750 mg per kg per day (23 times the human systemic exposure at the recommended dose of 200 mg per day in DESCOVY) or in rats at doses up to 600 mg per kg per day (28 times the human systemic exposure at the recommended dose in DESCOVY).

FTC was not genotoxic in the reverse mutation bacterial test (Ames test), mouse lymphoma or mouse micronucleus assays.

FTC did not affect fertility in male rats at approximately 140 times or in male and female mice at approximately 60 times higher exposures (AUC) than in humans given the recommended 200 mg daily dosage in DESCOVY. Fertility was normal in the offspring of mice exposed daily from before birth (in utero) through sexual maturity at daily exposures (AUC) of approximately 60 times higher than human exposures at the recommended 200 mg daily dosage in DESCOVY.

Tenofovir Alafenamide

Since TAF is rapidly converted to tenofovir and a lower tenofovir exposure in rats and mice was observed after TAF administration compared to TDF administration, carcinogenicity studies were conducted only with TDF. Long-term oral carcinogenicity studies of TDF in mice and rats were carried out at exposures up to approximately 10 times (mice) and 4 times (rats) those observed in humans at the recommended dose of TDF (300 mg) for HIV-1 infection. The tenofovir exposure in these studies was approximately 167 times (mice) and 55 times (rat) those observed in humans after administration of the daily recommended dose of DESCOVY. At the high dose in female mice, liver adenomas were increased at tenofovir exposures approximately 10 times (300 mg TDF) and 167 times (DESCOVY) the exposure observed in humans. In rats, the study was negative for carcinogenic findings.

TAF was not genotoxic in the reverse mutation bacterial test (Ames test), mouse lymphoma or rat micronucleus assays.

There were no effects on fertility, mating performance, or early embryonic development when TAF was administered to male rats at a dose equivalent to 62 times (25 mg TAF) the human dose based on body surface area comparisons for 28 days prior to mating and to female rats for 14 days prior to mating through Day 7 of gestation.

13.2 Animal Toxicology and/or Pharmacology

Minimal to slight infiltration of mononuclear cells in the posterior uvea was observed in dogs with similar severity after three- and nine-month administration of TAF; reversibility was seen after a three-month recovery period. No eye toxicity was observed in the dog at systemic exposures of 5 (TAF) and 15 (tenofovir) times the exposure seen in humans with the recommended daily TAF dose in DESCOVY.

14 CLINICAL STUDIES

14.1 Overview of Clinical Trials

The efficacy and safety of DESCOVY have been evaluated in the trials summarized in Table 17.

Table 17 Trials Conducted with FTC+TAF-Containing Products for HIV-1 Treatment and DESCOVY for HIV-1 PrEP
Trial | Population | Study Arms (N) | Timepoint
Study 104 [Randomized, double-blind, active-controlled study.] (NCT01780506) Study 111 (NCT01797445) | Treatment-naïve adults with HIV-1 | FTC+TAF with EVG+COBI [Administered as GENVOYA®.] (866) FTC+TDF with EVG+COBI [Administered as STRIBILD®.] (867) | 48 Weeks
Study 109 [Randomized, open-label, active controlled trial.] (NCT01815736) | Virologically-suppressed [HIV-1 RNA less than 50 copies per mL.] adults with HIV-1 | FTC+TAF with EVG+COBI (799) ATRIPLA® or TRUVADA®+ATV+COBI or ritonavir or FTC+TDF with EVG+COBI (397) | 48 Weeks
Study 112 [Open label trial.] (NCT01818596) | Virologically-suppressed adults with HIV-1 and renal impairment [Estimated creatinine clearance between 30 and 69 mL per minute by Cockcroft-Gault method.] | FTC+TAF with EVG+COBI (242) | 24 Weeks
Study 1825 (NCT02600819) | Virologically-suppressed adults with HIV-1 and ESRD [End stage renal disease (estimated creatinine clearance of less than 15 mL per minute by Cockcroft-Gault method).] receiving chronic hemodialysis | FTC+TAF with EVG+COBI (55) | 48 Weeks
Study 106 (Cohort 1) (NCT01854775) | Treatment-naïve adolescents with HIV-1 between the ages of 12 to less than 18 years (at least 35 kg) | FTC+TAF with EVG+COBI (50) | 48 Weeks
Study 106 (Cohort 2) (NCT01854775) | Virologically- suppressed children with HIV-1 between the ages of 6 to less than 12 years (at least 25 kg) | FTC+TAF with EVG+COBI (52) | 48 Weeks
Study 1474 (Cohort 3) (NCT02881320) | Virologically- suppressed children with HIV-1 at least 2 years (at least 14 kg and less than 25 kg) | FTC+TAF with bictegravir [Administered as BIKTARVY®.] (22) | 24 Weeks
Study 128 (Cohort 2) (NCT02016924) | Virologically- suppressed children with HIV-1 between the ages of 6 to less than 12 years (at least 25 kg and less than 40 kg) | DESCOVY with DRV+COBI (9) | 48 Weeks
Study 128 (Cohort 3) (NCT02016924) | Virologically- suppressed children with HIV-1 at least 2 years (at least 14 kg and less than 25 kg) | DESCOVY with DRV+COBI (11) | 48 Weeks
DISCOVER (NCT02842086) | Men or transgender women without HIV-1 who have sex with men | DESCOVY (2,670) TRUVADA® (2,665) | 4,370 person-years [Exposure in the DESCOVY group.]

14.2 Clinical Trial Results for Treatment of HIV-1

Clinical Trials in Adults with HIV-1

In trials of FTC+TAF with EVG+COBI in adults with HIV-1 as initial therapy in those with no antiretroviral treatment history (N=866) and to replace a stable antiretroviral regimen in those who were virologically-suppressed for at least 6 months with no known resistance substitutions (N=799), 92% and 96% of participants in the two populations, respectively, had HIV-1 RNA less than 50 copies per mL at Week 48.

Clinical Trials in Pediatric Patients with HIV-1

Study 106:

An open-label, single arm trial of FTC+TAF with EVG+COBI enrolled 50 treatment-naïve adolescents with HIV-1 aged 12 to less than 18 years weighing at least 35 kg (cohort 1) and 52 virologically suppressed children with HIV-1 aged 6 to less than 12 years weighing at least 25 kg (cohort 2). In cohort 1, the virologic response rate (i.e., HIV-1 RNA less than 50 copies per mL) was 92% (46/50) and the mean increase from baseline in CD4+ cell count was 224 cells per mm^3 at Week 48. In cohort 2, 98% (51/52) of participants remained virologically suppressed at Week 48. From a mean (SD) baseline CD4+ cell count of 961 (275.5) cells per mm^3, the mean change from baseline in CD4+ cell count was -66 cells per mm^3 and the mean (SD) change in CD4% was -0.6% (4.4%) at Week 48. All participants maintained CD4+ cell counts above 400 cells/mm^3 [see Adverse Reactions (6.1) and Use in Specific Populations (8.4)].

Study 1474:

In a separate open-label single arm trial of FTC+TAF with bictegravir that enrolled 24 virologically-suppressed children at least 2 years of age and weighing at least 14 to less than 25 kg (cohort 3), 91% (20/22) of participants remained virologically suppressed at Week 24. From a mean (SD) baseline CD4+ count of 1104 (440), the mean (SD) change from baseline in CD4+ cell count was −126 (264) cells per mm^3, and the mean (SD) change in CD4% was 0.2% (4.4%) at Week 24.

Study 128:

In a separate open-label trial DESCOVY was administered in combination with DRV+COBI to virologically-suppressed pediatric participants with HIV-1. In cohort 2 of this trial in 9 pediatric participants aged 6 to less than 12 years and weighing at least 25 to less than 40 kg, 100% (9/9) remained virologically-suppressed at Week 48. In cohort 2, from a mean (SD) baseline CD4+ count of 898 (209), the mean (SD) change from baseline in CD4+ cell count was 10 (199) cells per mm^3 and the mean (SD) change in CD4% was 1.26% (4.8%) at Week 48. In cohort 3 of this trial in 11 pediatric participants at least 2 years of age and weighing 14 to less than 25 kg, 91% (10/11) remained virologically-suppressed at Week 48.In cohort 3, from a mean (SD) CD4+ count of 1185 (317), the mean (SD) change from baseline in CD4+ cell count was -122 (329) cells per mm^3 and the mean (SD) change in CD4% was 1.4% (2.5%) at Week 48.

Clinical Trials in Adults with HIV-1 and Renal Insufficiency

In a trial in 248 adults with HIV-1 and estimated creatinine clearance greater than 30 mL per minute but less than 70 mL per minute, 95% (235/248) of the combined population of treatment-naïve participants began on FTC+TAF with EVG+COBI (N=6) and those previously virologically-suppressed on other regimens and switched to FTC+TAF with EVG+COBI (N=242) had HIV-1 RNA less than 50 copies per mL at Week 24.

In a trial in 55 virologically-suppressed adults with HIV-1 and ESRD (estimated creatinine clearance of less than 15 mL per minute) receiving chronic hemodialysis for at least 6 months who switched to FTC+TAF with EVG+COBI, 82% (45/55) maintained HIV-1 RNA less than 50 copies per mL at Week 48. Two participants had HIV-1 RNA ≥ 50 copies per mL by Week 48, 7 discontinued due to AE or other reasons while suppressed, and 1 did not have an HIV-1 RNA measurement at Week 48.

14.3 Clinical Trial Results for HIV-1 PrEP

The efficacy and safety of DESCOVY to reduce the risk of acquiring HIV-1 infection were evaluated in a randomized, double-blind multinational trial (DISCOVER) in HIV-seronegative men (N=5,262) or transgender women (N=73) who have sex with men and are at risk of HIV-1 infection, comparing once daily DESCOVY (N=2,670) to TRUVADA (FTC/TDF 200 mg/300 mg; N=2,665). Evidence of risk behavior at entry into the trial included at least one of the following: two or more unique condomless anal sex partners in the past 12 weeks or a diagnosis of rectal gonorrhea/chlamydia or syphilis in the past 24 weeks. The median age of participants was 34 years (range, 18-76); 84% were White, 9% Black/Mixed Black, 4% Asian, and 24% Hispanic/Latino. At baseline, 897 participants (17%) reported receiving TRUVADA for PrEP.

At weeks 4, 12, and every 12 weeks thereafter, all participants received local standard of care HIV-1 prevention services, including HIV-1 testing, evaluation of adherence, safety evaluations, risk-reduction counseling, condoms, management of sexually transmitted infections, and assessment of sexual behavior.

Trial participants maintained a high risk of sexual HIV-1 acquisition, with high rates of rectal gonorrhea (DESCOVY, 24%; TRUVADA, 25%), rectal chlamydia (DESCOVY, 30%; TRUVADA, 31%), and syphilis (14% in both treatment groups) during the trial.

The primary outcome was the incidence of documented HIV-1 infection per 100 person-years in participants randomized to DESCOVY and TRUVADA (with a minimum follow-up of 48 weeks and at least 50% of participants having 96 weeks of follow-up). DESCOVY was non-inferior to TRUVADA in reducing the risk of acquiring HIV-1 infection (Table 18). The results were similar across the subgroups of age, race, gender identity, and baseline TRUVADA for PrEP use.

Table 18 HIV-1 Infection Results in DISCOVER Trial – Full Analysis Set
 | DESCOVY (N=2,670) | TRUVADA (N=2,665) | Rate Ratio (95% CI)
 | 4,370 person-years | 4,386 person-years | Rate Ratio (95% CI)
HIV-1 infections, n | 7 | 15
Rate of HIV-1 infections per 100 person-years | 0.16 | 0.34 | 0.468 (0.19, 1.15)
CI = Confidence interval.

Of the 22 participants diagnosed with HIV-1 infection in the trial, five had suspected baseline infection prior to study entry (DESCOVY, 1; TRUVADA, 4). In a case-control substudy of intracellular drug levels and estimated number of daily doses as measured by dried blood spot testing, median intracellular tenofovir diphosphate concentrations were substantially lower in participants infected with HIV-1 at the time of diagnosis compared with uninfected matched control participants. For both DESCOVY and TRUVADA, efficacy was therefore strongly correlated to adherence to daily dosing.

16 HOW SUPPLIED/STORAGE AND HANDLING

DESCOVY tablets are available in bottles and blister packs containing 30 tablets:

Bottles

- 200 mg/25 mg tablets each contain 200 mg of emtricitabine (FTC) and 25 mg of tenofovir alafenamide (TAF). These tablets are blue, rectangular-shaped, and film-coated with “GSI” debossed on one side and “225” on the other side (NDC 61958-2002-1).
- 120 mg/15 mg tablets each contain 120 mg of FTC and 15 mg of TAF. These tablets are white, round-shaped, and film coated with “GSI” debossed on one side and “15” on the other side (NDC 61958-2005-1).

Bottles contain a silica gel desiccant, polyester coil, and child resistant closure.

Keep bottle tightly closed.

Blister Pack

- 200 mg/25 mg tablets each contain 200 mg of FTC and 25 mg of TAF. These tablets are blue, rectangular-shaped, and film-coated with “GSI” debossed on one side and “225” on the other side (NDC 61958-2002-2).

Blister packs are sealed with a child-resistant laminated foil lidding material (peel-push) and each blister cavity contains a die-cut desiccant film which is heat staked to the foil lidding material.

STORAGE AND HANDLING

Store at 25°C (77°F); excursions permitted to 15°C to 30°C (59°F to 86°F) (see USP Controlled Room Temperature).

Dispense only in original container.

17 PATIENT COUNSELING INFORMATION

Advise the patient to read the FDA-approved patient labeling (Medication Guide).

Important Information for Individuals Without HIV-1 Taking DESCOVY for HIV-1 PrEP

Advise individuals without HIV-1 about the following [see Warnings and Precautions (5.2)]:

- The need to confirm that they are HIV-negative before starting to take DESCOVY to reduce the risk of acquiring HIV-1.
- That HIV-1 resistance substitutions may emerge in individuals with undetected HIV-1 infection who are taking DESCOVY, because DESCOVY alone does not constitute a complete regimen for HIV-1 treatment.
- The importance of taking DESCOVY on a regular dosing schedule and strict adherence to the recommended dosing schedule to reduce the risk of acquiring HIV-1. Individuals without HIV-1 who miss doses are at greater risk of acquiring HIV-1 than those who do not miss doses.
- That DESCOVY does not prevent other sexually acquired infections and should be used as part of a complete prevention strategy including other prevention measures.
- To use condoms consistently and correctly to lower the chances of sexual contact with any body fluids such as semen, vaginal secretions, or blood.
- The importance of knowing their HIV-1 status and the HIV-1 status of their partner(s).
- The importance of virologic suppression in their partner(s) with HIV-1.
- The need to get tested regularly for HIV-1 (at least every 3 months, or more frequently for some individuals such as adolescents) and to ask their partner(s) to get tested as well.
- To report any symptoms of acute HIV-1 infection (flu-like symptoms) to their healthcare provider immediately.
- That the signs and symptoms of acute infection include fever, headache, fatigue, arthralgia, vomiting, myalgia, diarrhea, pharyngitis, rash, night sweats, and adenopathy (cervical and inguinal).
- To get tested for other sexually transmitted infections, such as syphilis, chlamydia, and gonorrhea, that may facilitate HIV-1 transmission.
- To assess their sexual risk behavior and get support to help reduce sexual risk behavior.

Post-treatment Acute Exacerbation of Hepatitis B in Patients with HBV

Inform individuals that severe acute exacerbations of hepatitis B have been reported in patients who are infected with HBV and have discontinued products containing FTC and/or TDF and may likewise occur with discontinuation of DESCOVY [see Warnings and Precautions (5.1)]. Advise individuals with HBV to not discontinue DESCOVY without first informing their healthcare provider.

Immune Reconstitution Syndrome

Advise patients with HIV-1 to inform their healthcare provider immediately of any symptoms of infection. In some patients with advanced HIV infection (AIDS), signs and symptoms of inflammation from previous infections may occur soon after anti-HIV treatment is started [see Warnings and Precautions (5.3)].

New Onset or Worsening Renal Impairment

Advise patients with HIV-1 and individuals without HIV-1 to avoid taking DESCOVY with concurrent or recent use of nephrotoxic agents. Postmarketing cases of renal impairment, including acute renal failure, have been reported [see Warnings and Precautions (5.4)].

Lactic Acidosis and Severe Hepatomegaly

Lactic acidosis and severe hepatomegaly with steatosis, including fatal cases, have been reported with use of drugs similar to DESCOVY. Advise patients with HIV-1 and individuals without HIV-1 that they should stop DESCOVY if they develop clinical symptoms suggestive of lactic acidosis or pronounced hepatotoxicity [see Warnings and Precautions (5.5)].

Dosage Recommendations for Treatment of HIV-1 Infection

Inform patients with HIV-1 that it is important to take DESCOVY with other antiretroviral drugs for the treatment of HIV-1 on a regular dosing schedule with or without food and to avoid missing doses as it can result in development of resistance [see Dosage and Administration (2.3, 2.4)].

Pregnancy Registry

Inform individuals using DESCOVY that there is an antiretroviral pregnancy registry to monitor fetal outcomes of pregnant women exposed to DESCOVY [see Use in Specific Populations (8.1)].

Lactation

Inform individuals with HIV-1 infection that the potential risks of breastfeeding include: (1) HIV-1 transmission to infants without HIV-1, (2) developing viral resistance in infants with HIV-1, and (3) adverse reactions in a breastfed infant similar to those seen in adults [see Use in Specific Populations (8.2)].

DESCOVY and TRUVADA are trademarks of Gilead Sciences, Inc., or its related companies. All other trademarks referenced herein are the property of their respective owners.

© 2025 Gilead Sciences, Inc. All rights reserved.

MEDICATION GUIDE
DESCOVY® (des-KOH-vee)
(emtricitabine and tenofovir alafenamide)
tablets

This Medication Guide provides information about two different ways that DESCOVY may be used. See the section “What is DESCOVY?” for detailed information about how DESCOVY may be used.

What is the most important information I should know about DESCOVY?
DESCOVY can cause serious side effects, including:

- Worsening of hepatitis B virus (HBV). Your healthcare provider will test you for HBV before or when you start treatment with DESCOVY. If you have HBV and take DESCOVY, your HBV may get worse (flare-up) if you stop taking DESCOVY. A “flare-up” is when your HBV suddenly returns in a worse way than before.
  - Do not run out of DESCOVY. Refill your prescription or talk to your healthcare provider before your DESCOVY is all gone.
  - Do not stop taking DESCOVY without first talking to your healthcare provider.
  - If you stop taking DESCOVY, your healthcare provider will need to check your health often and do blood tests regularly for several months to check your liver, and may give you a medicine to treat hepatitis B. Tell your healthcare provider about any new or unusual symptoms you may have after you stop taking DESCOVY.

For more information about side effects, see the section “What are the possible side effects of DESCOVY?”

Other important information for people who take DESCOVY to help reduce their risk of getting human immunodeficiency virus-1 (HIV-1), also called pre-exposure prophylaxis or “PrEP”:

Before taking DESCOVY to reduce your risk of getting HIV-1:

- You must be HIV-1 negative to start DESCOVY. You must get tested to make sure that you do not already have HIV-1.
- Do not take DESCOVY for HIV-1 PrEP unless you are confirmed to be HIV-1 negative.
- Some HIV-1 tests can miss HIV-1 in a person who has recently become infected. If you have flu-like symptoms, you could have recently become infected with HIV-1. Tell your healthcare provider if you had a flu-like illness within the last month before starting DESCOVY or at any time while taking DESCOVY. Symptoms of new HIV-1 include:

- tiredness
- fever
- joint or muscle aches
- headache
- sore throat

- vomiting or diarrhea
- rash
- night sweats
- enlarged lymph nodes in the neck or groin

While you are taking DESCOVY for HIV-1 PrEP:

- DESCOVY does not prevent other sexually transmitted infections (STIs). Practice safer sex by using a latex or polyurethane condom to reduce the risk of getting STIs.
- You must stay HIV-1 negative to keep taking DESCOVY for HIV-1 PrEP.
  - Know your HIV-1 status and the HIV-1 status of your partners.
  - Ask your partners with HIV-1 if they are taking HIV-1 medicines and have an undetectable viral load. An undetectable viral load is when the amount of virus in the blood is too low to be measured in a lab test. To maintain an undetectable viral load, your partners must keep taking HIV-1 medicines every day. Your risk of getting HIV-1 is lower if your partners with HIV-1 are taking effective treatment.
  - Get tested for HIV-1 at least every 3 months or when your healthcare provider tells you.
  - Get tested for other STIs such as syphilis, chlamydia, and gonorrhea. These infections make it easier for HIV-1 to infect you.
  - If you think you were exposed to HIV-1, tell your healthcare provider right away. They may want to do more tests to be sure you are still HIV-1 negative.
  - Get information and support to help reduce sexual risk behaviors.
  - Do not miss any doses of DESCOVY. Missing doses increases your risk of getting HIV-1.
- If you do become HIV-1 positive, you need more medicine than DESCOVY alone to treat HIV-1. DESCOVY by itself is not a complete treatment for HIV-1.

If you have HIV-1 and take only DESCOVY, over time your HIV-1 may become harder to treat.

What is DESCOVY?
DESCOVY is a prescription medicine that may be used in two different ways. DESCOVY is used:

- to treat HIV-1
  - in adults and children who weigh at least 77 pounds (35 kg) together with other HIV-1 medicines.
  - in children who weigh at least 31 pounds (14 kg) and less than 77 pounds (35 kg) together with certain other HIV-1 medicines. Your healthcare provider will determine which other HIV-1 medicines may be used with DESCOVY.
- for HIV-1 PrEP to reduce the risk of getting HIV-1 in adults and adolescents who weigh at least 77 pounds (35 kg). It is not known if DESCOVY is effective in reducing the risk of getting HIV-1 from certain types of sex.
  - DESCOVY for PrEP is not for use in people born female (assigned female at birth) who are at risk of getting HIV-1 from vaginal sex, because its effectiveness has not been studied.

HIV-1 is the virus that causes Acquired Immune Deficiency Syndrome (AIDS).
DESCOVY contains the prescription medicines emtricitabine and tenofovir alafenamide.
It is not known if DESCOVY for treatment of HIV-1 is safe and effective in children who weigh less than 31 pounds (14 kg).
It is not known if DESCOVY is safe and effective in reducing the risk of HIV-1 in people who weigh less than 77 pounds (35 kg).

For people taking DESCOVY for HIV-1 PrEP:
Do not take DESCOVY for HIV-1 PrEP if:

- you already have HIV-1. If you are HIV-1 positive, you need to take other medicines with DESCOVY to treat HIV-1. DESCOVY by itself is not a complete treatment for HIV-1.
- you do not know your HIV-1 status. You may already be HIV-1 positive. You need to take other HIV-1 medicines with DESCOVY to treat HIV-1.

DESCOVY can only help reduce your risk of getting HIV-1 before you are infected.

What should I tell my healthcare provider before taking DESCOVY?
Before taking DESCOVY, tell your healthcare provider about all of your medical conditions, including if you:

- have liver problems, including HBV
- have kidney problems
- are pregnant or plan to become pregnant. It is not known if DESCOVY can harm your unborn baby. Tell your healthcare provider if you become pregnant during treatment with DESCOVY.
  Pregnancy Registry: There is a pregnancy registry for people who take DESCOVY during pregnancy. The purpose of this registry is to collect information about the health of you and your baby. Talk with your healthcare provider about how you can take part in this registry.
- are breastfeeding or plan to breastfeed. DESCOVY passes to your baby in your breast milk. Talk to your healthcare provider about the following risks to your baby from breastfeeding during treatment with DESCOVY:
  - the HIV-1 virus may pass to your baby if your baby does not have HIV-1.
  - the HIV-1 virus may become harder to treat if your baby has HIV-1.
  - your baby may get side effects from DESCOVY.

Tell your healthcare provider about all the medicines you take, including prescription and over-the-counter medicines, vitamins, and herbal supplements.
Some medicines may interact with DESCOVY. Keep a list of your medicines and show it to your healthcare provider and pharmacist when you get a new medicine.

- You can ask your healthcare provider or pharmacist for a list of medicines that interact with DESCOVY.
- Do not start a new medicine without telling your healthcare provider. Your healthcare provider can tell you if it is safe to take DESCOVY with other medicines.

How should I take DESCOVY?

- Take DESCOVY exactly as your healthcare provider tells you to take it. If you take DESCOVY to treat HIV-1, you need to take DESCOVY with other HIV-1 medicines. Your healthcare provider will tell you what medicines to take and how to take them.
- Take DESCOVY 1 time each day with or without food.
- If you are on dialysis, take your daily dose of DESCOVY following dialysis.
- Do not change your dose or stop taking DESCOVY without first talking with your healthcare provider. Stay under a healthcare provider’s care when taking DESCOVY. Do not miss a dose of DESCOVY.
- If you take too much DESCOVY, call your healthcare provider or go to the nearest hospital emergency room right away.
- When your DESCOVY supply starts to run low, get more from your healthcare provider or pharmacy.
  - If you are taking DESCOVY for treatment of HIV-1, the amount of virus in your blood may increase if the medicine is stopped for even a short time. The virus may develop resistance to DESCOVY and become harder to treat.
  - If you are taking DESCOVY for HIV-1 PrEP, missing doses increases your risk of getting HIV-1.

What are the possible side effects of DESCOVY?
DESCOVY may cause serious side effects, including:

- See “What is the most important information I should know about DESCOVY?”
- Changes in your immune system (Immune Reconstitution Syndrome) can happen when you start taking medicines to treat HIV-1. Your immune system may get stronger and begin to fight infections that have been hidden in your body for a long time. Tell your healthcare provider right away if you have any new symptoms of infection after starting your HIV-1 medicine.
- New or worse kidney problems, including kidney failure. Your healthcare provider should do blood and urine tests to check your kidneys before you start and while taking DESCOVY. Your healthcare provider may tell you to stop taking DESCOVY if you develop new or worse kidney problems.
- Too much lactic acid in your blood (lactic acidosis). Too much lactic acid is a serious but rare medical emergency that can lead to death. Tell your healthcare provider right away if you get these symptoms: weakness or being more tired than usual, unusual muscle pain, being short of breath or fast breathing, stomach pain with nausea and vomiting, cold or blue hands and feet, feel dizzy or lightheaded, or a fast or abnormal heartbeat.
- Severe liver problems. In rare cases, severe liver problems can happen that can lead to death. Tell your healthcare provider right away if you get these symptoms: skin or the white part of your eyes turns yellow, dark “tea-colored” urine, light-colored stools, loss of appetite for several days or longer, nausea, or stomach-area pain.

The most common side effect of DESCOVY for treatment of HIV-1 is nausea.
The most common side effect of DESCOVY for HIV-1 PrEP is diarrhea.
These are not all of the possible side effects of DESCOVY.
Call your doctor for medical advice about side effects. You may report side effects to FDA at 1-800-FDA-1088.

How should I store DESCOVY?

- Store DESCOVY at room temperature between 68°F to 77°F (20°C to 25°C).
- Keep DESCOVY in its original bottle or blister pack.
- Keep the bottle tightly closed.

Keep DESCOVY and all medicines out of reach of children.

General information about the safe and effective use of DESCOVY.
Medicines are sometimes prescribed for purposes other than those listed in a Medication Guide. Do not use DESCOVY for a condition for which it was not prescribed. Do not give DESCOVY to other people, even if they have the same symptoms you have. It may harm them. You can ask your healthcare provider or pharmacist for information about DESCOVY that is written for health professionals.

What are the ingredients in DESCOVY?
Active ingredients: emtricitabine and tenofovir alafenamide.
Inactive ingredients: croscarmellose sodium, magnesium stearate, and microcrystalline cellulose.
The 200 mg/25 mg tablets are film-coated with a coating material containing indigo carmine aluminum lake, polyethylene glycol, polyvinyl alcohol, talc, and titanium dioxide. The 120 mg/15 mg tablets are film-coated with a coating material containing polyvinyl alcohol, titanium dioxide, polyethylene glycol, and talc.
Manufactured and distributed by: Gilead Sciences, Inc. Foster City, CA 94404
DESCOVY is a trademark of Gilead Sciences, Inc., or its related companies. All other trademarks referenced herein are the property of their respective owners.
© 2025 Gilead Sciences, Inc. All rights reserved.
208215-GS-010
For more information, call 1-800-445-3235 or go to www.DESCOVY.com.

This Medication Guide has been approved by the U.S. Food and Drug Administration

Revised: 06/2025

PRINCIPAL DISPLAY PANEL - 200 mg/25 mg Tablet Bottle Label

NDC 61958- 2002-1
30 tablets

Descovy ®
(emtricitabine and tenofovir
alafenamide) Tablets

200 mg/25 mg

Note to pharmacist: Do not cover ALERT box with pharmacy label.

ALERT: Find out about medicines that
should NOT be taken with Discovy ®

PRINCIPAL DISPLAY PANEL - 30 Tablet Blister Pack

NDC 61958-2002-2
30 tablet blister pack

Descovy®
(emtricitabine and
tenofovir alafenamide) tablets
200 mg / 25 mg

Rx only

Note to pharmacist:
Do not cover ALERT box with pharmacy label.

ALERT: Find out about medicines that
should NOT be taken with Descovy

PRINCIPAL DISPLAY PANEL - 120 mg/15 mg Tablet Bottle Label

NDC 61958-2005-1
30 tablets

Descovy®
(emtricitabine and
tenofovir alafenamide)
tablets

120 mg/15 mg

Note to pharmacist:
Do not cover ALERT box with pharmacy label.

ALERT: Find out about medicines that
should NOT be taken with Descovy